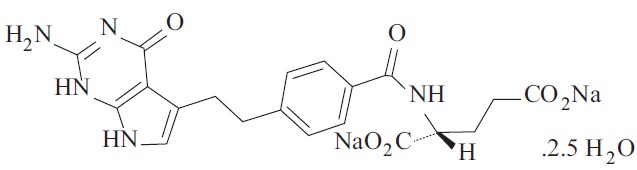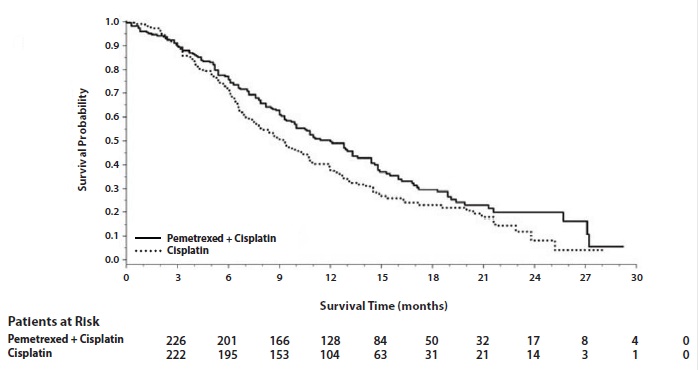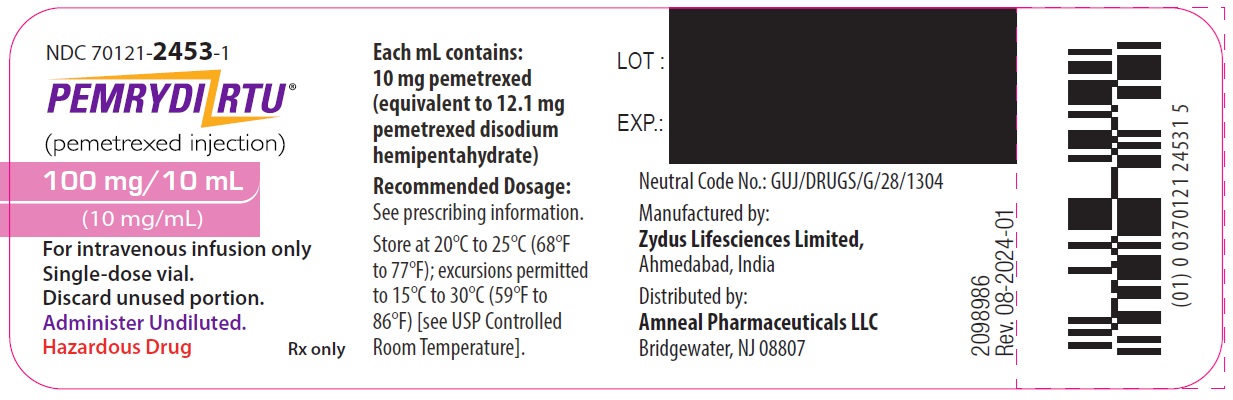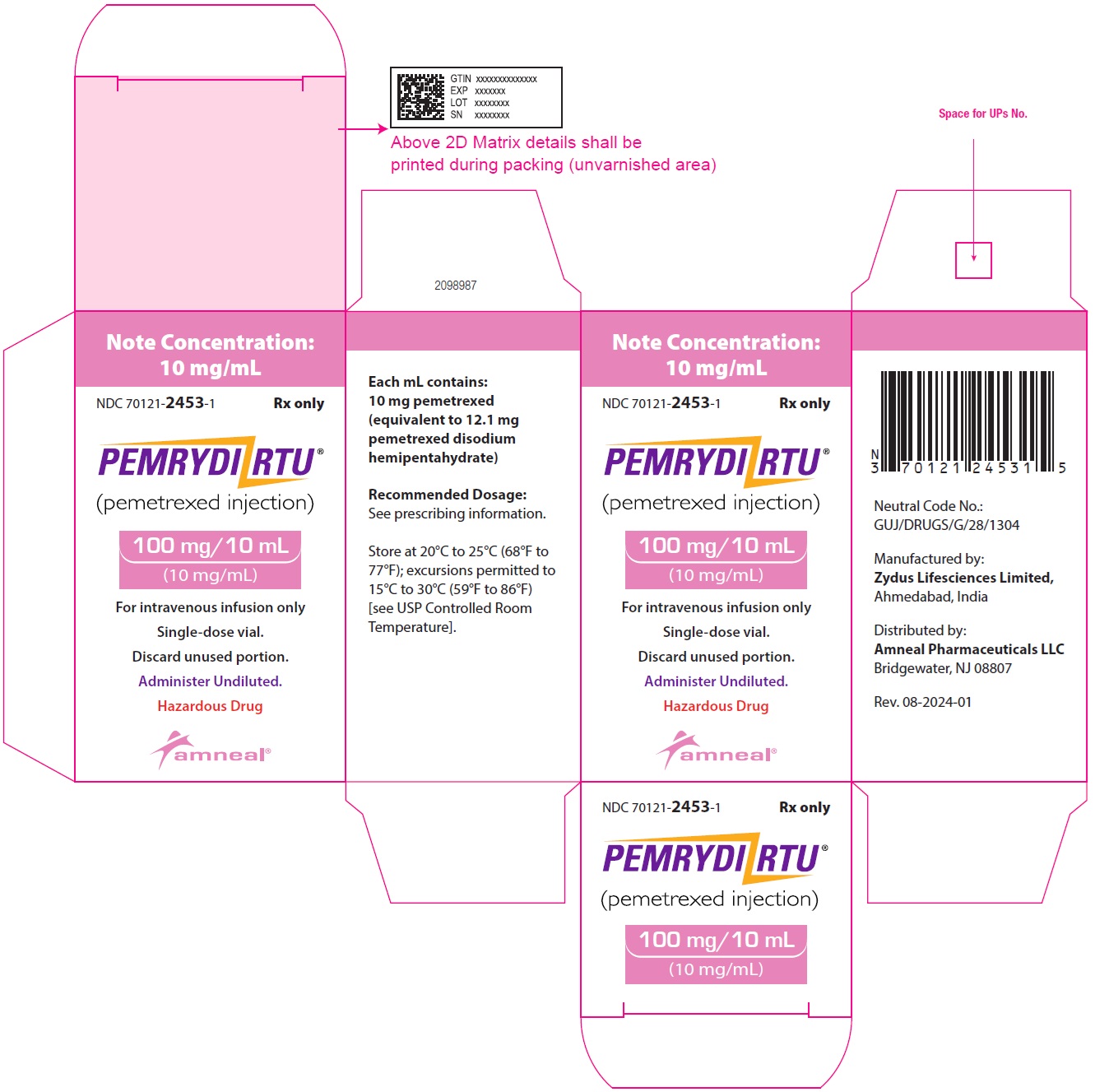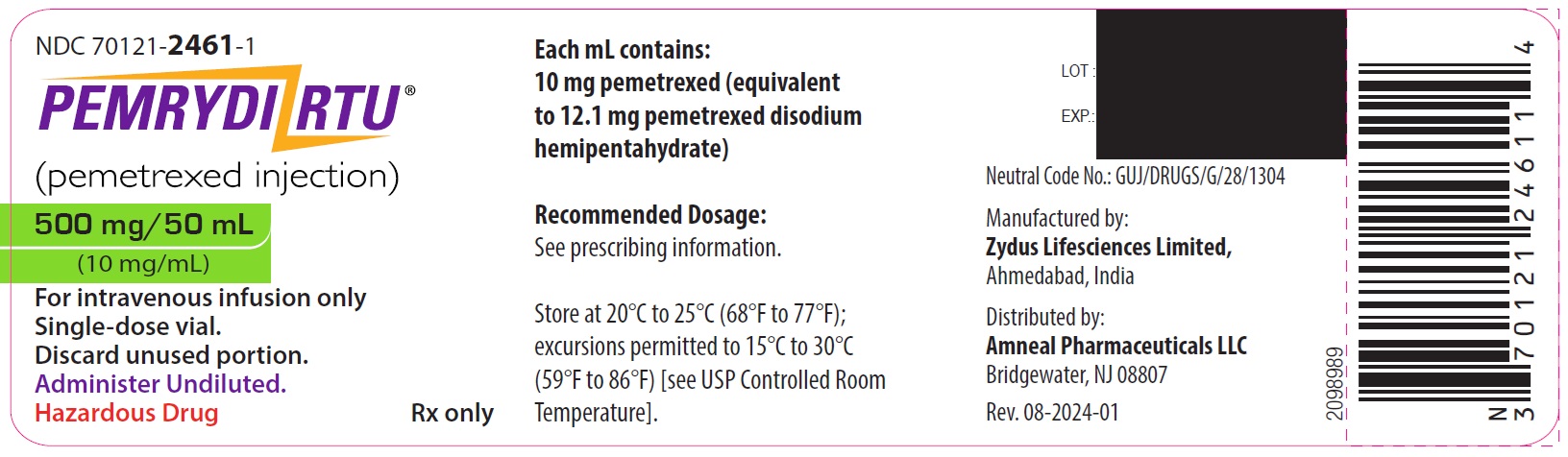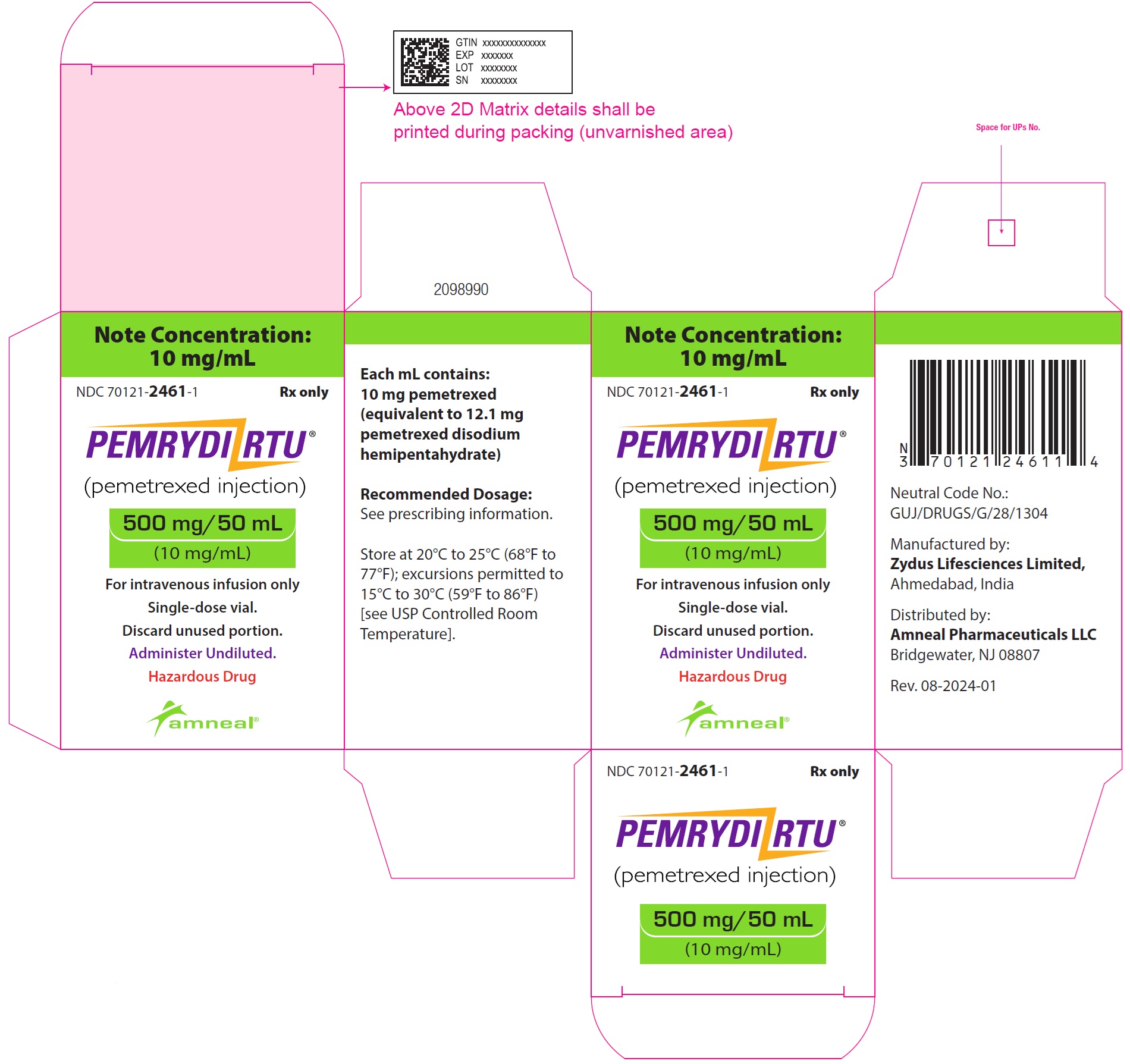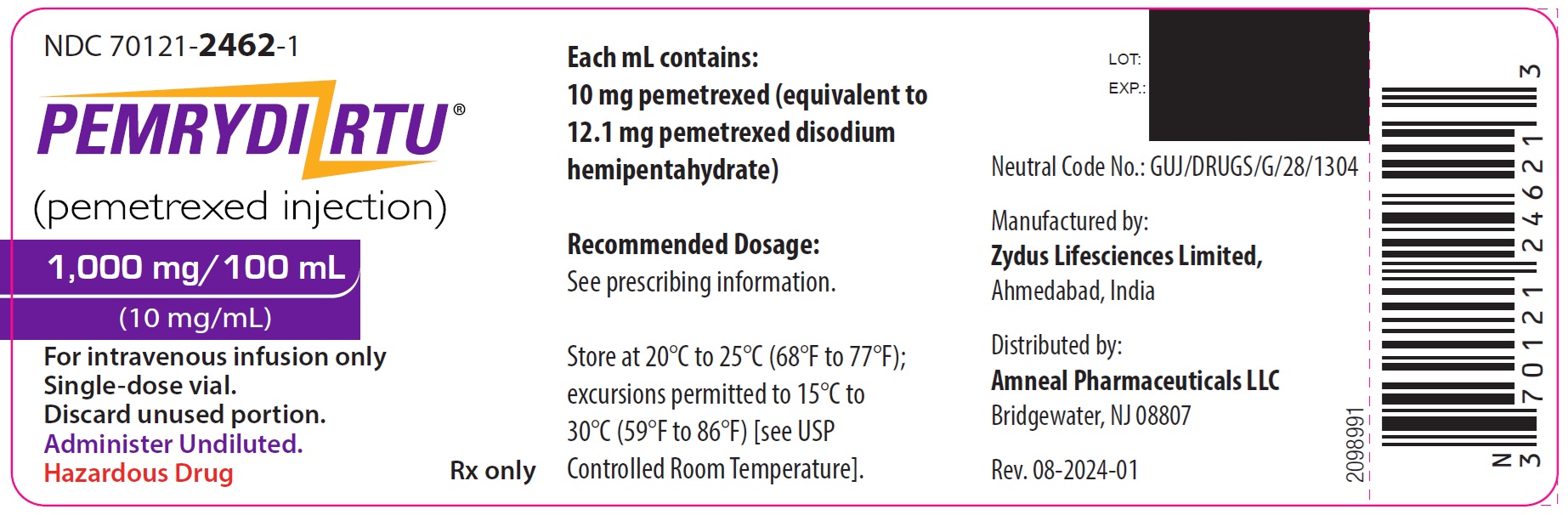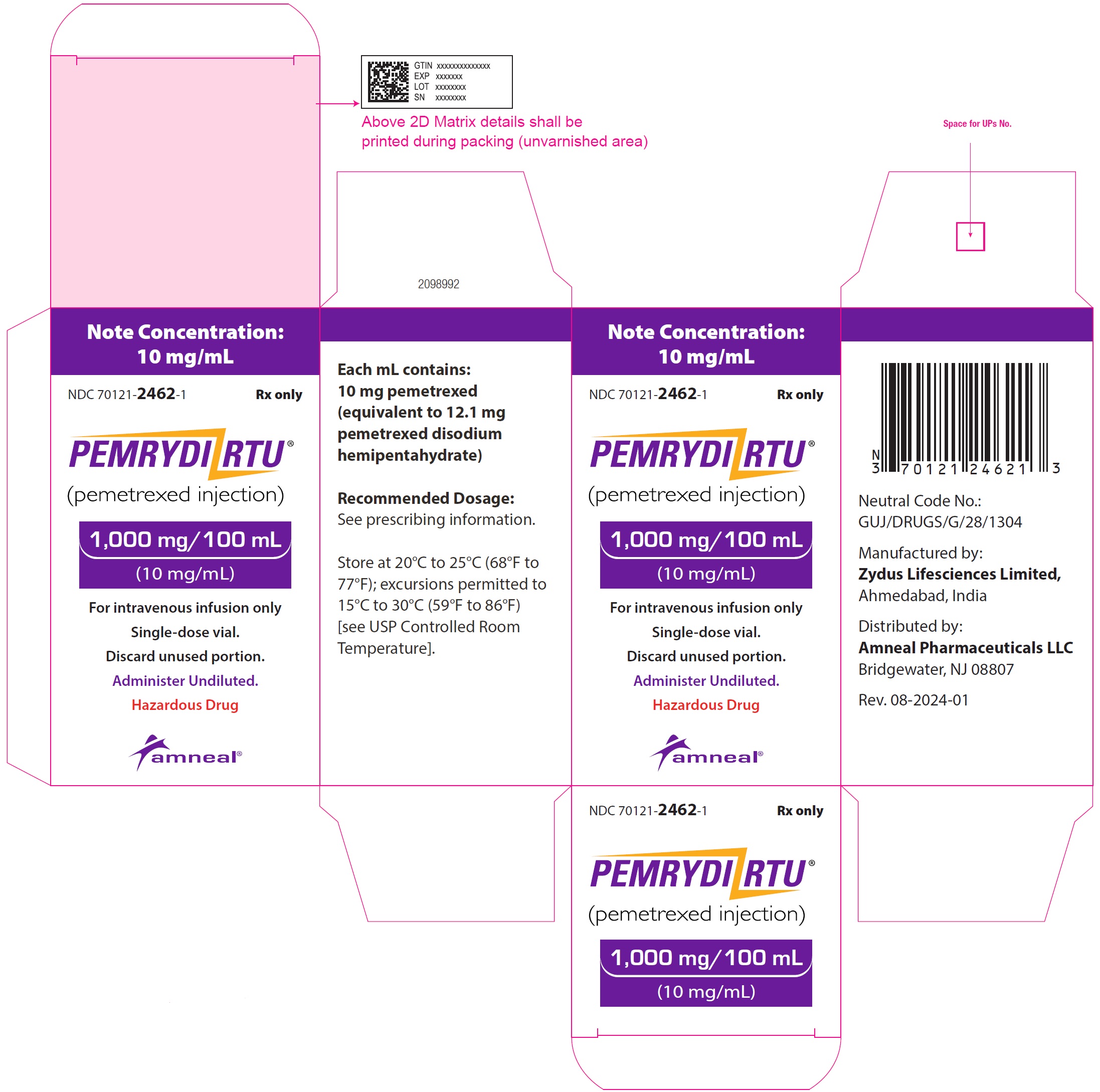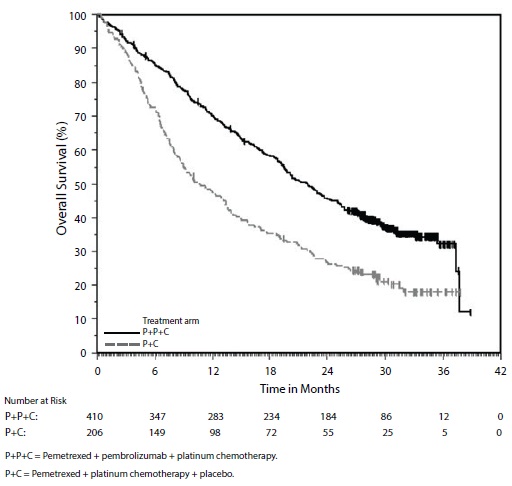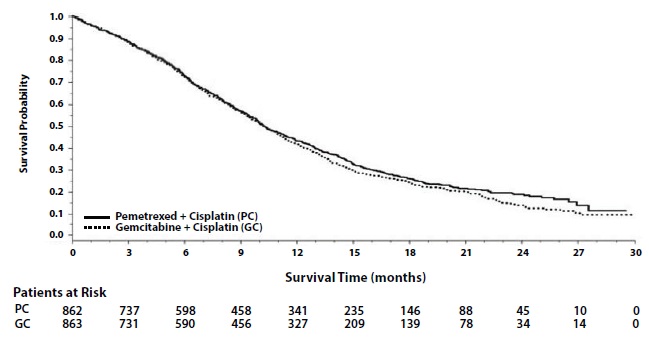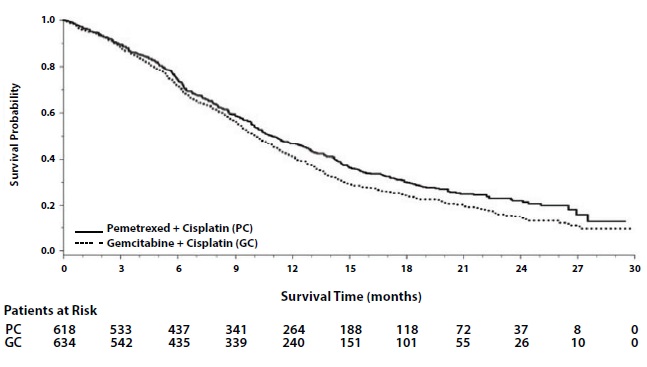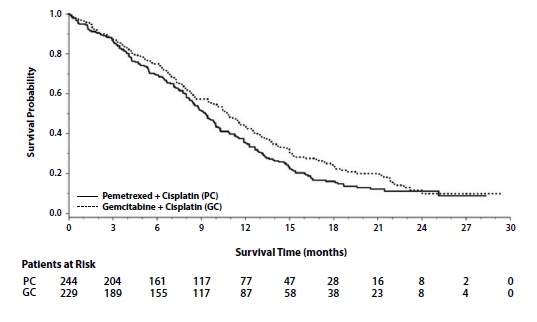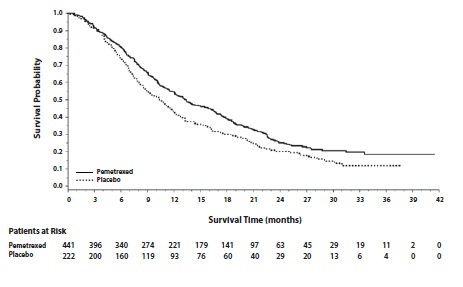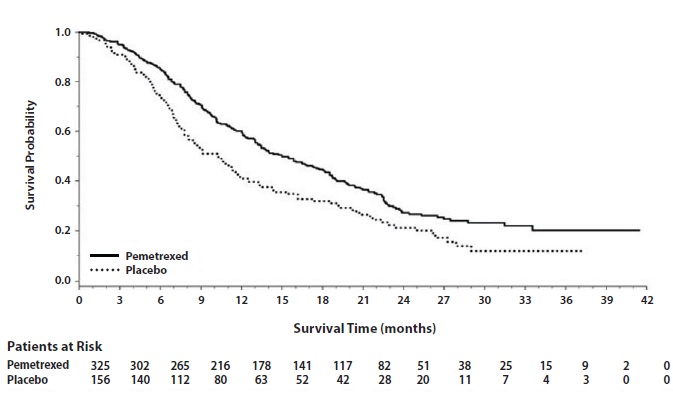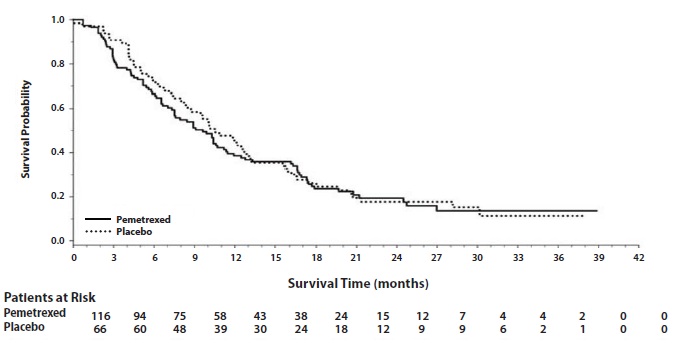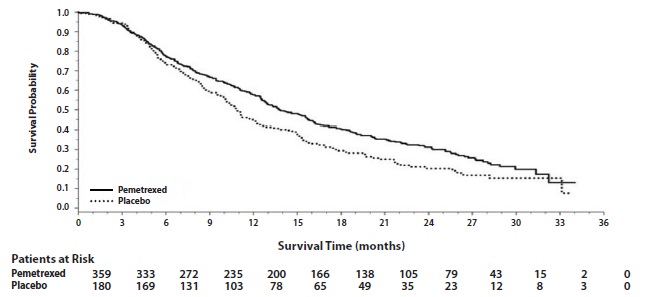 DRUG LABEL: PEMRYDI RTU
NDC: 70121-2453 | Form: INJECTION
Manufacturer: Amneal Pharmaceuticals LLC
Category: prescription | Type: HUMAN PRESCRIPTION DRUG LABEL
Date: 20250708

ACTIVE INGREDIENTS: PEMETREXED DISODIUM HEMIPENTAHYDRATE 100 mg/10 mL
INACTIVE INGREDIENTS: MANNITOL; SODIUM CHLORIDE; CYSTEINE HYDROCHLORIDE; SODIUM HYDROXIDE; HYDROCHLORIC ACID

HIGHLIGHTS OF PRESCRIBING INFORMATION

These highlights do not include all the information needed to use PEMRYDI RTU safely and effectively. See full prescribing information for PEMRYDI RTU.
PEMRYDI RTU (pemetrexed injection), for intravenous use
Initial U.S. Approval: 2004

RECENT MAJOR CHANGES

Dosage and Administration, Preparation for Administration (2.7) 11/2024

1. INDICATIONS AND USAGE

PEMRYDI RTU® is a folate analog metabolic inhibitor indicated:

- in combination with pembrolizumab and platinum chemotherapy, for the initial treatment of patients with metastatic non-squamous non-small cell lung cancer (NSCLC), with no EGFR or ALK genomic tumor aberrations. (1.1)
- in combination with cisplatin for the initial treatment of patients with locally advanced or metastatic, non-squamous NSCLC. (1.1)
- as a single agent for the maintenance treatment of patients with locally advanced or metastatic, non-squamous NSCLC whose disease has not progressed after four cycles of platinum-based first-line chemotherapy. (1.1)
- as a single agent for the treatment of patients with recurrent, metastatic non-squamous, NSCLC after prior chemotherapy. (1.1)
  Limitations of Use: PEMRYDI RTU is not indicated for the treatment of patients with squamous cell, non-small cell lung cancer. (1.1)
- initial treatment, in combination with cisplatin, of patients with malignant pleural mesothelioma whose disease is unresectable or who are otherwise not candidates for curative surgery. (1.2)

2. DOSAGE AND ADMINISTRATION

- The recommended dose of PEMRYDI RTU administered with pembrolizumab and platinum chemotherapy in patients with a creatinine clearance (calculated by Cockcroft-Gault equation) of 45 mL/min or greater is 500 mg/m^2 as an intravenous infusion over 10 minutes, administered after pembrolizumab and prior to platinum chemotherapy, on Day 1 of each 21-day cycle. (2.1)
- The recommended dose of PEMRYDI RTU, administered as a single agent or with cisplatin, in patients with creatinine clearance of 45 mL/minute or greater is 500 mg/m^2 as an intravenous infusion over 10 minutes on Day 1 of each 21-day cycle. (2.1, 2.2)
- Initiate folic acid 400 mcg to 1,000 mcg orally, once daily, beginning 7 days prior to the first dose of PEMRYDI RTU and continue until 21 days after the last dose of PEMRYDI RTU. (2.4)
- Administer vitamin B12, 1 mg intramuscularly, 1 week prior to the first dose of PEMRYDI RTU and every 3 cycles. (2.4)
- Administer dexamethasone 4 mg orally, twice daily the day before, the day of, and the day after PEMRYDI RTU administration. (2.4)

3. DOSAGE FORMS AND STRENGTHS

- Injection: 100 mg/10 mL, 500 mg/50 mL, 1,000 mg/100 mL in single dose vials (3)

4. CONTRAINDICATIONS

History of severe hypersensitivity reaction to pemetrexed. (4)

5. WARNINGS AND PRECAUTIONS

- Myelosuppression: Can cause severe bone marrow suppression resulting in cytopenia and an increased risk of infection. Do not administer PEMRYDI RTU when the absolute neutrophil count is less than 1,500 cells/mm^3 and platelets are less than 100,000 cells/mm^3. Initiate supplementation with oral folic acid and intramuscular vitamin B12 to reduce the severity of hematologic and gastrointestinal toxicity of PEMRYDI RTU. (2.4, 5.1)
- Renal Failure: Can cause severe, and sometimes fatal, renal failure. Do not administer when creatinine clearance is less than 45 mL/min. (2.3, 5.2)
- Bullous and Exfoliative Skin Toxicity: Permanently discontinue for severe and life-threatening bullous, blistering or exfoliating skin toxicity. (5.3)
- Interstitial Pneumonitis: Withhold for acute onset of new or progressive unexplained pulmonary symptoms. Permanently discontinue if pneumonitis is confirmed. (5.4)
- Radiation Recall: Can occur in patients who received radiation weeks to years previously; permanently discontinue for signs of radiation recall. (5.5)
- Embryo-Fetal Toxicity: Can cause fetal harm. Advise patients of the potential risk to a fetus and to use effective contraception. (5.7, 8.1, 8.3)

6. ADVERSE REACTIONS

- The most common adverse reactions (incidence ≥ 20%) of pemetrexed, when administered as a single agent are fatigue, nausea, and anorexia. (6.1)

- The most common adverse reactions (incidence ≥ 20%) of pemetrexed when administered with cisplatin are vomiting, neutropenia, anemia, stomatitis/pharyngitis, thrombocytopenia, and constipation. (6.1)

- The most common adverse reactions (incidence ≥ 20%) of pemetrexed when administered in combination with pembrolizumab and platinum chemotherapy are fatigue/asthenia, nausea, constipation, diarrhea, decreased appetite, rash, vomiting, cough, dyspnea, and pyrexia. (6.1)

To report SUSPECTED ADVERSE REACTIONS, contact Amneal Pharmaceuticals LLC at 1-877-835-5472 or FDA at 1-800-FDA-1088 or www.fda.gov/medwatch.

7. DRUG INTERACTIONS

Ibuprofen increased risk of PEMRYDI RTU toxicity in patients with mild to moderate renal impairment. Modify the ibuprofen dosage as recommended for patients with a creatinine clearance between 45 mL/min and 79 mL/min. (2.5, 5.6, 7)

8. USE IN SPECIFIC POPULATIONS

Lactation: Advise not to breastfeed. (8.2)

FULL PRESCRIBING INFORMATION

1. INDICATIONS AND USAGE

1.1 Non-Squamous Non-Small Cell Lung Cancer (NSCLC)

PEMRYDI RTU® is indicated:

- in combination with pembrolizumab and platinum chemotherapy, for the initial treatment of patients with metastatic non-squamous non-small cell lung cancer (NSCLC), with no EGFR or ALK genomic tumor aberrations.
- in combination with cisplatin for the initial treatment of patients with locally advanced or metastatic, non-squamous NSCLC.
- as a single agent for the maintenance treatment of patients with locally advanced or metastatic, non-squamous NSCLC whose disease has not progressed after four cycles of platinum-based first-line chemotherapy.
- as a single agent for the treatment of patients with recurrent, metastatic non-squamous, NSCLC after prior chemotherapy.

Limitations of Use: PEMRYDI RTU is not indicated for the treatment of patients with squamous cell, non-small cell lung cancer [see Clinical Studies (14.1)].

1.2 Mesothelioma

PEMRYDI RTU is indicated, in combination with cisplatin, for the initial treatment of patients with malignant pleural mesothelioma whose disease is unresectable or who are otherwise not candidates for curative surgery.

2. DOSAGE AND ADMINISTRATION

2.1 Recommended Dosage for Non-Squamous NSCLC

- The recommended dose of PEMRYDI RTU when administered with pembrolizumab and platinum chemotherapy for the initial treatment of metastatic non-squamous NSCLC in patients with a creatinine clearance (calculated by Cockcroft-Gault equation) of 45 mL/min or greater is 500 mg/m^2 as an intravenous infusion over 10 minutes administered after pembrolizumab and prior to carboplatin or cisplatin on Day 1 of each 21-day cycle for 4 cycles. Following completion of platinum-based therapy, treatment with PEMRYDI RTU with or without pembrolizumab is administered until disease progression or unacceptable toxicity. Please refer to the full prescribing information for pembrolizumab and for carboplatin or cisplatin.
- The recommended dose of PEMRYDI RTU when administered with cisplatin for initial treatment of locally advanced or metastatic non-squamous NSCLC in patients with a creatinine clearance (calculated by Cockcroft-Gault equation) of 45 mL/min or greater is 500 mg/m^2 as an intravenous infusion over 10 minutes administered prior to cisplatin on Day 1 of each 21-day cycle for up to six cycles in the absence of disease progression or unacceptable toxicity.
- The recommended dose of PEMRYDI RTU for maintenance treatment of non-squamous NSCLC in patients with a creatinine clearance (calculated by Cockcroft-Gault equation) of 45 mL/min or greater is 500 mg/m^2 as an intravenous infusion over 10 minutes on Day 1 of each 21-day cycle until disease progression or unacceptable toxicity after four cycles of platinum-based first-line chemotherapy.
- The recommended dose of PEMRYDI RTU for treatment of recurrent non-squamous NSCLC in patients with a creatinine clearance (calculated by Cockcroft-Gault equation) of 45 mL/min or greater is 500 mg/m^2 as an intravenous infusion over 10 minutes on Day 1 of each 21-day cycle until disease progression or unacceptable toxicity.

2.2 Recommended Dosage for Mesothelioma

- The recommended dose of PEMRYDI RTU when administered with cisplatin in patients with a creatinine clearance (calculated by Cockcroft-Gault equation) of 45 mL/min or greater is 500 mg/m^2 as an intravenous infusion over 10 minutes on Day 1 of each 21-day cycle until disease progression or unacceptable toxicity.

2.3 Renal Impairment

- PEMRYDI RTU dosing recommendations are provided for patients with a creatinine clearance (calculated by Cockcroft-Gault equation) of 45 mL/min or greater [see Dosage and Administration (2.1, 2.2)]. There is no recommended dose for patients whose creatinine clearance is less than 45 mL/min [see Use in Specific Populations (8.6)].

2.4 Premedication and Concomitant Medications to Mitigate Toxicity

Vitamin Supplementation

- Initiate folic acid 400 mcg to 1,000 mcg orally once daily, beginning 7 days before the first dose of PEMRYDI RTU and continuing until 21 days after the last dose of PEMRYDI RTU [see Warnings and Precautions (5.1)].
- Administer vitamin B12, 1 mg intramuscularly, 1 week prior to the first dose of PEMRYDI RTU and every 3 cycles thereafter. Subsequent vitamin B12 injections may be given the same day as treatment with PEMRYDI RTU [see Warnings and Precautions (5.1)]. Do not substitute oral vitamin B12 for intramuscular vitamin B12.

Corticosteroids

- Administer dexamethasone 4 mg orally twice daily for three consecutive days, beginning the day before each PEMRYDI RTU administration.

2.5 Dosage Modification of Ibuprofen in Patients with Mild to Moderate Renal Impairment Receiving PEMRYDI RTU

In patients with creatinine clearances between 45 mL/min and 79 mL/min, modify administration of ibuprofen as follows [see Warnings and Precautions (5.6), Drug Interactions (7) and Clinical Pharmacology (12.3)]:

- Avoid administration of ibuprofen for 2 days before, the day of, and 2 days following administration of PEMRYDI RTU.
- Monitor patients more frequently for myelosuppression, renal, and gastrointestinal toxicity, if concomitant administration of ibuprofen cannot be avoided.

2.6 Dosage Modifications for Adverse Reactions

Obtain complete blood count on Days 1, 8, and 15 of each cycle. Assess creatinine clearance prior to each cycle. Do not administer PEMRYDI RTU if the creatinine clearance is less than 45 mL/min.

Delay initiation of the next cycle of PEMRYDI RTU until:

- recovery of non-hematologic toxicity to Grade 0-2,
- absolute neutrophil count (ANC) is 1,500 cells/mm^3 or higher, and
- platelet count is 100,000 cells/mm^3 or higher.

Upon recovery, modify the dosage of PEMRYDI RTU in the next cycle as specified in Table 1.

For dosing modifications for cisplatin, carboplatin, or pembrolizumab, refer to their prescribing information.

Table 1: Recommended Dosage Modifications for Adverse Reactionsa

Toxicity in Most Recent Treatment Cycle | PEMRYDI RTU Dose Modification for Next Cycle
Myelosuppressive toxicity [see Warnings and Precautions (5.1)]
ANC less than 500/mm^3 and platelets greater than or equal to 50,000/mm^3 OR Platelet count less than 50,000/mm^3 without bleeding. | 75% of previous dose
Platelet count less than 50,000/mm^3 with bleeding | 50% of previous dose
Recurrent Grade 3 or 4 myelosuppression after 2 dose reductions | Discontinue
Non-hematologic toxicity
Any Grade 3 or 4 toxicities EXCEPT mucositis or neurologic toxicity OR Diarrhea requiring hospitalization | 75% of previous dose
Grade 3 or 4 mucositis | 50% of previous dose
Renal toxicity [see Warnings and Precautions (5.2)] | Withhold until creatinine clearance is 45 mL/min or greater
Grade 3 or 4 neurologic toxicity | Permanently discontinue
Recurrent Grade 3 or 4 non-hematologic toxicity after 2 dose reductions | Permanently discontinue
Severe and life-threatening Skin Toxicity [see Warnings and Precautions (5.3)] | Permanently discontinue
Interstitial Pneumonitis [see Warnings and Precautions (5.4)] | Permanently discontinue
a National Cancer Institute Common Toxicity Criteria for Adverse Events version 2 (NCI CTCAE v2).

2.7 Preparation for Administration

PEMRYDI RTU is a hazardous drug. Follow applicable special handling and disposal procedures.^1

- Calculate the dose of PEMRYDI RTU and determine the volume of needed PEMRYDI RTU. Each vial contains an excess of PEMRYDI RTU to facilitate delivery of labeled amount.
- Withdraw the calculated dose of PEMRYDI RTU from the vial(s) and discard the vial(s) with any unused portion.
- Transfer the calculated dose into an empty intravenous bag. Do NOT further dilute PEMRYDI RTU.
- Visually inspect for particulate matter and discoloration prior to administration. Discard if particulate matter or discoloration is observed.
- Immediately administer PEMRYDI RTU undiluted, as an intravenous infusion over 10 minutes using an infusion pump.
- If not used immediately, store undiluted PEMRYDI RTU solution in infusion bag for no more than 24 hours at controlled room temperature of 20°C to 25°C (68°F to 77°F) [see USP Controlled Room Temperature]. Discard the infusion bag solution if not used within 24 hours.

3. DOSAGE FORMS AND STRENGTHS

Injection: PEMRYDI RTU is a sterile clear colorless to pale yellow to greenish yellow solution available as follows:

- 100 mg/10 mL (10 mg/mL) single-dose vial
- 500 mg/50 mL (10 mg/mL) single-dose vial
- 1,000 mg/100 mL (10 mg/mL) single-dose vial

4. CONTRAINDICATIONS

PEMRYDI RTU is contraindicated in patients with a history of severe hypersensitivity reaction to pemetrexed [see Adverse Reactions (6.1)].

5. WARNINGS AND PRECAUTIONS

5.1 Myelosuppression and Increased Risk of Myelosuppression without Vitamin Supplementation

Pemetrexed can cause severe myelosuppression resulting in a requirement for transfusions and which may lead to neutropenic infection. The risk of myelosuppression is increased in patients who do not receive vitamin supplementation. In Study JMCH, incidences of Grade 3-4 neutropenia (38% versus 23%), thrombocytopenia (9% versus 5%), febrile neutropenia (9% versus 0.6%), and neutropenic infection (6% versus 0) were higher in patients who received pemetrexed plus cisplatin without vitamin supplementation as compared to patients who were fully supplemented with folic acid and vitamin B12 prior to and throughout pemetrexed plus cisplatin treatment.

Initiate supplementation with oral folic acid and intramuscular vitamin B12 prior to the first dose of PEMRYDI RTU; continue vitamin supplementation during treatment and for 21 days after the last dose of PEMRYDI RTU to reduce the severity of hematologic and gastrointestinal toxicity of PEMRYDI RTU [see Dosage and Administration (2.4)]. Obtain a complete blood count at the beginning of each cycle. Do not administer PEMRYDI RTU until the ANC is at least 1,500 cells/mm^3 and platelet count is at least 1,00,000 cells/mm^3. Permanently reduce PEMRYDI RTU in patients with an ANC of less than 500 cells/mm^3 or platelet count of less than 50,000 cells/mm^3 in previous cycles [see Dosage and Administration (2.6)].

In Studies JMDB and JMCH, among patients who received vitamin supplementation, incidence of Grade 3-4 neutropenia was 15% and 23%, the incidence of Grade 3-4 anemia was 6% and 4%, and incidence of Grade 3-4 thrombocytopenia was 4% and 5%, respectively. In Study JMCH, 18% of patients in the pemetrexed arm required red blood cell transfusions compared to 7% of patients in the cisplatin arm [see Adverse Reactions (6.1)]. In Studies JMEN, PARAMOUNT, and JMEI, where all patients received vitamin supplementation, incidence of Grade 3-4 neutropenia ranged from 3% to 5%, and incidence of Grade 3-4 anemia ranged from 3% to 5%.

5.2 Renal Failure

Pemetrexed can cause severe, and sometimes fatal, renal toxicity. The incidences of renal failure in clinical studies in which patients received pemetrexed with cisplatin were 2.1% in Study JMDB and 2.2% in Study JMCH. The incidence of renal failure in clinical studies in which patients received pemetrexed as a single agent ranged from 0.4% to 0.6% (Studies JMEN, PARAMOUNT, and JMEI [see Adverse Reactions (6.1)]. Determine creatinine clearance before each dose and periodically monitor renal function during treatment with PEMRYDI RTU. Withhold PEMRYDI RTU in patients with a creatinine clearance of less than 45 mL/minute [see Dosage and Administration (2.3)].

5.3 Bullous and Exfoliative Skin Toxicity

Serious and sometimes fatal, bullous, blistering and exfoliative skin toxicity, including cases suggestive of Stevens-Johnson Syndrome/Toxic epidermal necrolysis can occur with pemetrexed. Permanently discontinue pemetrexed for severe and life-threatening bullous, blistering or exfoliating skin toxicity.

5.4 Interstitial Pneumonitis

Serious interstitial pneumonitis, including fatal cases, can occur with pemetrexed treatment. Withhold pemetrexed for acute onset of new or progressive unexplained pulmonary symptoms such as dyspnea, cough, or fever pending diagnostic evaluation. If pneumonitis is confirmed, permanently discontinue pemetrexed.

5.5 Radiation Recall

Radiation recall can occur with pemetrexed in patients who have received radiation weeks to years previously. Monitor patients for inflammation or blistering in areas of previous radiation treatment. Permanently discontinue pemetrexed for signs of radiation recall.

5.6 Increased Risk of Toxicity with Ibuprofen in Patients with Renal Impairment

Exposure to pemetrexed is increased in patients with mild to moderate renal impairment who take concomitant ibuprofen, increasing the risks of adverse reactions of pemetrexed. In patients with creatinine clearances between 45 mL/min and 79 mL/min, avoid administration of ibuprofen for 2 days before, the day of, and 2 days following administration of pemetrexed. If concomitant ibuprofen use cannot be avoided, monitor patients more frequently for pemetrexed adverse reactions, including myelosuppression, renal, and gastrointestinal toxicity [see Dosage and Administration (2.5), Drug Interactions (7) and Clinical Pharmacology (12.3)].

5.7 Embryo-Fetal Toxicity

Based on findings from animal studies and its mechanism of action, pemetrexed can cause fetal harm when administered to a pregnant woman. In animal reproduction studies, intravenous administration of pemetrexed to pregnant mice during the period of organogenesis was teratogenic, resulting in developmental delays and increased malformations at doses lower than the recommended human dose of 500 mg/m^2. Advise pregnant women of the potential risk to a fetus. Advise females of reproductive potential to use effective contraception during treatment with PEMRYDI RTU and for 6 months after the last dose. Advise males with female partners of reproductive potential to use effective contraception during treatment with PEMRYDI RTU and for 3 months after the last dose [see Use in Specific Populations (8.1, 8.3) and Clinical Pharmacology (12.1)].

6. ADVERSE REACTIONS

The following adverse reactions are discussed in greater detail in other sections of the labeling:

- Myelosuppression [see Warnings and Precautions (5.1)]
- Renal failure [see Warnings and Precautions (5.2)]
- Bullous and exfoliative skin toxicity [see Warning and Precautions (5.3)]
- Interstitial pneumonitis [see Warnings and Precautions (5.4)]
- Radiation recall [see Warnings and Precautions (5.5)]

6.1 Clinical Trials Experience

Because clinical trials are conducted under widely varying conditions, adverse reactions rates cannot be directly compared to rates in other clinical trials and may not reflect the rates observed in clinical practice.

In clinical trials, the most common adverse reactions (incidence ≥ 20%) of pemetrexed, when administered as a single agent, are fatigue, nausea, and anorexia. The most common adverse reactions (incidence ≥ 20 %) of pemetrexed, when administered in combination with cisplatin are vomiting, neutropenia, anemia, stomatitis/pharyngitis, thrombocytopenia, and constipation. The most common adverse reactions (incidence ≥ 20%) of pemetrexed, when administered in combination with pembrolizumab and platinum chemotherapy, are fatigue/asthenia, nausea, constipation, diarrhea, decreased appetite, rash, vomiting, cough, dyspnea, and pyrexia.

Non-Squamous NSCLC

First-line Treatment of Metastatic Non-squamous NSCLC with Pembrolizumab and Platinum Chemotherapy

The safety of pemetrexed, in combination with pembrolizumab and investigator’s choice of platinum (either carboplatin or cisplatin), was investigated in Study KEYNOTE-189, a multicenter, double-blind, randomized (2:1), active-controlled trial in patients with previously untreated, metastatic non-squamous NSCLC with no EGFR or ALK genomic tumor aberrations. A total of 607 patients received pemetrexed, pembrolizumab, and platinum every 3 weeks for 4 cycles followed by pemetrexed and pembrolizumab (n=405), or placebo, pemetrexed, and platinum every 3 weeks for 4 cycles followed by placebo and pemetrexed (n=202). Patients with autoimmune disease that required systemic therapy within 2 years of treatment; a medical condition that required immunosuppression; or who had received more than 30 Gy of thoracic radiation within the prior 26 weeks were ineligible [see Clinical Studies (14.1)].

The median duration of exposure to pemetrexed was 7.2 months (range: 1 day to 1.7 years). Seventy-two percent of patients received carboplatin. The study population characteristics were: median age of 64 years (range: 34 to 84), 49% age 65 years or older, 59% male, 94% White and 3% Asian, and 18% with history of brain metastases at baseline.

Pemetrexed was discontinued for adverse reactions in 23% of patients in the pemetrexed, pembrolizumab, and platinum arm. The most common adverse reactions resulting in discontinuation of pemetrexed in this arm were acute kidney injury (3%) and pneumonitis (2%). Adverse reactions leading to interruption of pemetrexed occurred in 49% of patients in the pemetrexed, pembrolizumab, and platinum arm. The most common adverse reactions or laboratory abnormalities leading to interruption of pemetrexed in this arm (≥ 2%) were neutropenia (12%), anemia (7%), asthenia (4%), pneumonia (4%), thrombocytopenia (4%), increased blood creatinine (3%), diarrhea (3%), and fatigue (3%).

Table 2 summarizes the adverse reactions that occurred in ≥ 20% of patients treated with pemetrexed, pembrolizumab, and platinum.

Table 2: Adverse Reactions Occurring in ≥ 20% of Patients in KEYNOTE-189

 | Pemetrexed; Pembrolizumab; Platinum Chemotherapy; n=405 |  | Placebo; Pemetrexed; Platinum Chemotherapy; n=202
Adverse Reaction | All Gradesa; (%) | Grade 3-4 (%) | All Grades; (%) | Grade 3-4 (%)
Gastrointestinal Disorders
Nausea | 56 | 3.5 | 52 | 3.5
Constipation | 35 | 1.0 | 32 | 0.5
Diarrhea | 31 | 5 | 21 | 3.0
Vomiting | 24 | 3.7 | 23 | 3.0
General Disorders and Administration Site Conditions
Fatigueb | 56 | 12 | 58 | 6
Pyrexia | 20 | 0.2 | 15 | 0
Metabolism and Nutrition Disorders
Decreased appetite | 28 | 1.5 | 30 | 0.5
Skin and Subcutaneous Tissue Disorders
Rashc | 25 | 2.0 | 17 | 2.5
Respiratory, Thoracic and Mediastinal Disorders
Cough | 21 | 0 | 28 | 0
Dyspnea | 21 | 3.7 | 26 | 5
a Graded per NCI CTCAE version 4.03.
b Includes asthenia and fatigue.
c Includes genital rash, rash, rash generalized, rash macular, rash maculo-papular, rash papular, rash pruritic, and rash pustular.

Table 3 summarizes the laboratory abnormalities that worsened from baseline in at least 20% of patients treated with pemetrexed, pembrolizumab, and platinum.

Table 3: Laboratory Abnormalities Worsened from Baseline in ≥ 20% of Patients in KEYNOTE-189

 | Pemetrexed Pembrolizumab Platinum Chemotherapy |  | Placebo Pemetrexed Platinum Chemotherapy
Laboratory Testa | All Gradesb % | Grades 3-4 % | All Grades % | Grades 3-4 %
Chemistry
Hyperglycemia | 63 | 9 | 60 | 7
Increased ALT | 47 | 3.8 | 42 | 2.6
Increased AST | 47 | 2.8 | 40 | 1.0
Hypoalbuminemia | 39 | 2.8 | 39 | 1.1
Increased creatinine | 37 | 4.2 | 25 | 1.0
Hyponatremia | 32 | 7 | 23 | 6
Hypophosphatemia | 30 | 10 | 28 | 14
Increased alkaline phosphatase | 26 | 1.8 | 29 | 2.1
Hypocalcemia | 24 | 2.8 | 17 | 0.5
Hyperkalemia | 24 | 2.8 | 19 | 3.1
Hypokalemia | 21 | 5 | 20 | 5
Hematology
Anemia | 85 | 17 | 81 | 18
Lymphopenia | 64 | 22 | 64 | 25
Neutropenia | 48 | 20 | 41 | 19
Thrombocytopenia | 30 | 12 | 29 | 8
a Each test incidence is based on the number of patients who had both baseline and at least one on-study laboratory measurement available: pemetrexed/pembrolizumab/platinum chemotherapy (range: 381 to 401 patients) and placebo/pemetrexed/platinum chemotherapy (range: 184 to 197 patients).
b Graded per NCI CTCAE version 4.03.

Initial Treatment in Combination with Cisplatin

The safety of pemetrexed was evaluated in Study JMDB, a randomized (1:1), open-label, multicenter trial conducted in chemotherapy-naive patients with locally advanced or metastatic NSCLC. Patients received either pemetrexed 500 mg/m^2 intravenously and cisplatin 75 mg/m^2 intravenously on Day 1 of each 21-day cycle (n=839) or gemcitabine 1,250 mg/m^2 intravenously on Days 1 and 8 and cisplatin 75 mg/m^2 intravenously on Day 1 of each 21-day cycle (n=830). All patients were fully supplemented with folic acid and vitamin B12.

Study JMDB excluded patients with an Eastern Cooperative Oncology Group Performance Status (ECOG PS of 2 or greater), uncontrolled third-space fluid retention, inadequate bone marrow reserve and organ function, or a calculated creatinine clearance less than 45 mL/min. Patients unable to stop using aspirin or other non-steroidal anti-inflammatory drugs or unable to take folic acid, vitamin B12 or corticosteroids were also excluded from the study.

The data described below reflect exposure to pemetrexed plus cisplatin in 839 patients in Study JMDB. Median age was 61 years (range 26-83 years); 70% of patients were men; 78% were White, 16% were Asian, 2.9% were Hispanic or Latino, 2.1% were Black or African American, and <1% were other ethnicities; 36% had an ECOG PS 0. Patients received a median of 5 cycles of pemetrexed.

Table 4 provides the frequency and severity of adverse reactions that occurred in ≥ 5% of 839 patients receiving pemetrexed in combination with cisplatin in Study JMDB. Study JMDB was not designed to demonstrate a statistically significant reduction in adverse reaction rates for pemetrexed, as compared to the control arm, for any specified adverse reaction listed in Table 4.

Table 4: Adverse Reactions Occurring in ≥ 5% of Fully Vitamin-Supplemented Patients Receiving Pemetrexed in Combination with Cisplatin Chemotherapy in Study JMDB

Adverse Reactiona | Pemetrexed/Cisplatin (N=839) |  | Gemcitabine/Cisplatin (N=830)
Adverse Reactiona | All Grades (%) | Grade 3-4 (%) | All Grades (%) | Grade 3-4 (%)
All adverse reactions | 90 | 37 | 91 | 53
Laboratory
Hematologic
Anemia | 33 | 6 | 46 | 10
Neutropenia | 29 | 15 | 38 | 27
Thrombocytopenia | 10 | 4 | 27 | 13
Renal
Elevated creatinine | 10 | 1 | 7 | 1
Clinical
Gastrointestinal
Nausea | 56 | 7 | 53 | 4
Vomiting | 40 | 6 | 36 | 6
Anorexia | 27 | 2 | 24 | 1
Constipation | 21 | 1 | 20 | 0
Stomatitis/pharyngitis | 14 | 1 | 12 | 0
Diarrhea | 12 | 1 | 13 | 2
Dyspepsia/heartburn | 5 | 0 | 6 | 0
Constitutional symptoms
Fatigue | 43 | 7 | 45 | 5
Dermatology/Skin
Alopecia | 12 | 0 | 21 | 1
Rash/Desquamation | 7 | 0 | 8 | 1
Neurology
Sensory neuropathy | 9 | 0 | 12 | 1
Taste disturbance | 8 | 0 | 9 | 0
a NCI CTCAE version 2.0.

The following additional adverse reactions were observed in patients assigned to receive pemetrexed.

Incidence 1% to < 5%

Body as a Whole — febrile neutropenia, infection, pyrexia

General Disorders — dehydration

Metabolism and Nutrition — increased AST, increased ALT

Renal —renal failure

Eye Disorder — conjunctivitis

Incidence < 1%

Cardiovascular — arrhythmia

General Disorders — chest pain

Metabolism and Nutrition — increased GGT

Neurology — motor neuropathy

Maintenance Treatment Following First-line Non-Pemetrexed Containing Platinum-Based Chemotherapy

In Study JMEN, the safety of pemetrexed was evaluated in a randomized (2:1), placebo-controlled, multicenter trial conducted in patients with non-progressive locally advanced or metastatic NSCLC following four cycles of a first-line, platinum-based chemotherapy regimen. Patients received either pemetrexed 500 mg/m^2 or matching placebo intravenously every 21 days until disease progression or unacceptable toxicity. Patients in both study arms were fully supplemented with folic acid and vitamin B12.

Study JMEN excluded patients with an ECOG PS of 2 or greater, uncontrolled third-space fluid retention, inadequate bone marrow reserve and organ function, or a calculated creatinine clearance less than 45 mL/min. Patients unable to stop using aspirin or other non-steroidal anti-inflammatory drugs or unable to take folic acid, vitamin B12 or corticosteroids were also excluded from the study.

The data described below reflect exposure to pemetrexed in 438 patients in Study JMEN. Median age was 61 years (range 26-83 years), 73% of patients were men; 65% were White, 31% were Asian, 2.9% were Hispanic or Latino, and < 2% were other ethnicities; 39% had an ECOG PS 0. Patients received a median of 5 cycles of pemetrexed and a relative dose intensity of pemetrexed of 96%. Approximately half the patients (48%) completed at least six, 21-day cycles and 23% completed ten or more 21-day cycles of pemetrexed.

Table 5 provides the frequency and severity of adverse reactions reported in ≥ 5% of the 438 pemetrexed-treated patients in Study JMEN.

Table 5: Adverse Reactions Occurring in ≥ 5% of Patients Receiving Pemetrexed in Study JMEN

Adverse Reactiona | Pemetrexed (N=438) |  | Placebo (N=218)
Adverse Reactiona | All Grades (%) | Grade 3-4 (%) | All Grades (%) | Grade 3-4 (%)
All adverse reactions | 66 | 16 | 37 | 4
Laboratory
Hematologic
Anemia | 15 | 3 | 6 | 1
Neutropenia | 6 | 3 | 0 | 0
Hepatic
Increased ALT | 10 | 0 | 4 | 0
Increased AST | 8 | 0 | 4 | 0
Clinical
Constitutional symptoms
Fatigue | 25 | 5 | 11 | 1
Gastrointestinal
Nausea | 19 | 1 | 6 | 1
Anorexia | 19 | 2 | 5 | 0
Vomiting | 9 | 0 | 1 | 0
Mucositis/stomatitis | 7 | 1 | 2 | 0
Diarrhea | 5 | 1 | 3 | 0
Dermatology/Skin
Rash/desquamation | 10 | 0 | 3 | 0
Neurology
Sensory neuropathy | 9 | 1 | 4 | 0
Infection | 5 | 2 | 2 | 0
a NCI CTCAE version 3.0.

The requirement for transfusions (9.5% versus 3.2%), primarily red blood cell transfusions, and for erythropoiesis stimulating agents (5.9% versus 1.8%) were higher in the pemetrexed arm compared to the placebo arm.

The following additional adverse reactions were observed in patients who received pemetrexed.

Incidence 1% to <5%

Dermatology/Skin — alopecia, pruritus/itching

Gastrointestinal — constipation

General Disorders — edema, fever

Hematologic — thrombocytopenia

Eye Disorder — ocular surface disease (including conjunctivitis), increased lacrimation

Incidence <1%

Cardiovascular — supraventricular arrhythmia

Dermatology/Skin — erythema multiforme

General Disorders — febrile neutropenia, allergic reaction/hypersensitivity

Neurology — motor neuropathy

Renal — renal failure

Maintenance Treatment Following First-line Pemetrexed Plus Platinum Chemotherapy

The safety of pemetrexed was evaluated in PARAMOUNT, a randomized (2:1), placebo-controlled study conducted in patients with non-squamous NSCLC with non-progressive (stable or responding disease) locally advanced or metastatic NSCLC following four cycles of pemetrexed in combination with cisplatin as first-line therapy for NSCLC. Patients were randomized to receive pemetrexed 500 mg/m^2 or matching placebo intravenously on Day 1 of each 21-day cycle until disease progression or unacceptable toxicity. Patients in both study arms received folic acid and vitamin B12 supplementation.

PARAMOUNT excluded patients with an ECOG PS of 2 or greater, uncontrolled third-space fluid retention, inadequate bone marrow reserve and organ function, or a calculated creatinine clearance less than 45 mL/min. Patients unable to stop using aspirin or other non-steroidal anti-inflammatory drugs or unable to take folic acid, vitamin B12 or corticosteroids were also excluded from the study.

The data described below reflect exposure to pemetrexed in 333 patients in PARAMOUNT. Median age was 61 years (range 32 to 83 years); 58% of patients were men; 94% were White, 4.8% were Asian, and < 1% were Black or African American; 36% had an ECOG PS 0. The median number of maintenance cycles was 4 for pemetrexed and placebo arms. Dose reductions for adverse reactions occurred in 3.3% of patients in the pemetrexed arm and 0.6% in the placebo arm. Dose delays for adverse reactions occurred in 22% of patients in the pemetrexed arm and 16% in the placebo arm.

Table 6 provides the frequency and severity of adverse reactions reported in ≥ 5% of the 333 pemetrexed-treated patients in PARAMOUNT.

Table 6: Adverse Reactions Occurring in ≥ 5% of Patients Receiving Pemetrexed in PARAMOUNT

Adverse Reactiona | Pemetrexed (N=333) |  | Placebo (N=167)
Adverse Reactiona | All Grades (%) | Grade 3-4 (%) | All Grades (%) | Grades 3-4 (%)
All adverse reactions | 53 | 17 | 34 | 4.8
Laboratory
Hematologic
Anemia | 15 | 4.8 | 4.8 | 0.6
Neutropenia | 9 | 3.9 | 0.6 | 0
Clinical
Constitutional symptoms
Fatigue | 18 | 4.5 | 11 | 0.6
Gastrointestinal
Nausea | 12 | 0.3 | 2.4 | 0
Vomiting | 6 | 0 | 1.8 | 0
Mucositis/stomatitis | 5 | 0.3 | 2.4 | 0
General disorders
Edema | 5 | 0 | 3.6 | 0
a NCI CTCAE version 3.0.

The requirement for red blood cell (13% versus 4.8%) and platelet (1.5% versus 0.6%) transfusions, erythropoiesis stimulating agents (12% versus 7%), and granulocyte colony stimulating factors (6% versus 0%) were higher in the pemetrexed arm compared to the placebo arm.

The following additional Grade 3 or 4 adverse reactions were observed more frequently in the pemetrexed arm.

Incidence 1% to <5%

Blood/Bone Marrow — thrombocytopenia

General Disorders — febrile neutropenia

Incidence <1%

Cardiovascular — ventricular tachycardia, syncope

General Disorders — pain

Gastrointestinal — gastrointestinal obstruction

Neurologic — depression

Renal — renal failure

Vascular — pulmonary embolism

Treatment of Recurrent Disease After Prior Chemotherapy

The safety of pemetrexed was evaluated in Study JMEI, a randomized (1:1), open-label, active-controlled trial conducted in patients who had progressed following platinum-based chemotherapy. Patients received pemetrexed 500 mg/m^2 intravenously or docetaxel 75 mg/m^2 intravenously on Day 1 of each 21-day cycle. All patients on the pemetrexed arm received folic acid and vitamin B12 supplementation.

Study JMEI excluded patients with an ECOG PS of 3 or greater, uncontrolled third-space fluid retention, inadequate bone marrow reserve and organ function, or a calculated creatinine clearance less than 45 mL/min. Patients unable to discontinue aspirin or other non-steroidal anti-inflammatory drugs or unable to take folic acid, vitamin B12 or corticosteroids were also excluded from the study.

The data described below reflect exposure to pemetrexed in 265 patients in Study JMEI. Median age was 58 years (range 22 to 87 years); 73% of patients were men; 70% were White, 24% were Asian, 2.6% were Black or African American, 1.8% were Hispanic or Latino, and < 2% were other ethnicities; 19% had an ECOG PS 0.

Table 7 provides the frequency and severity of adverse reactions reported in ≥ 5% of the 265 pemetrexed-treated patients in Study JMEI. Study JMEI is not designed to demonstrate a statistically significant reduction in adverse reaction rates for pemetrexed, as compared to the control arm, for any specified adverse reaction listed in the Table 7 below.

Table 7: Adverse Reactions Occurring in ≥ 5% of Fully Supplemented Patients Receiving Pemetrexed in Study JMEI

Adverse Reactiona | Pemetrexed (N=265) |  | Docetaxel (N=276)
Adverse Reactiona | All Grades (%) | Grades 3-4 (%) | All Grade (%) | Grades 3-4 (%)
Laboratory
Hematologic
Anemia | 19 | 4 | 22 | 4
Neutropenia | 11 | 5 | 45 | 40
Thrombocytopenia | 8 | 2 | 1 | 0
Hepatic
Increased ALT | 8 | 2 | 1 | 0
Increased AST | 7 | 1 | 1 | 0
Clinical
Constitutional symptoms
Fatigue | 34 | 5 | 36 | 5
Fever | 8 | 0 | 8
Gastrointestinal
Nausea | 31 | 3 | 17 | 2
Anorexia | 22 | 2 | 24 | 3
Vomiting | 16 | 2 | 12 | 1
Stomatitis/pharyngitis | 15 | 1 | 17 | 1
Diarrhea | 13 | 0 | 24 | 3
Constipation | 6 | 0 | 4 | 0
Dermatology/Skin
Rash/desquamation | 14 | 0 | 6 | 0
Pruritus | 7 | 0 | 2 | 0
Alopecia | 6 | 1 | 38 | 2
a NCI CTCAE version 2.0.

The following additional adverse reactions were observed in patients assigned to receive pemetrexed.

Incidence 1% to <5%

Body as a Whole — abdominal pain, allergic reaction/hypersensitivity, febrile neutropenia, infection

Dermatology/Skin — erythema multiforme

Neurology — motor neuropathy, sensory neuropathy

Incidence <1%

Cardiovascular — supraventricular arrhythmias

Renal — renal failure

Mesothelioma

The safety of pemetrexed was evaluated in Study JMCH, a randomized (1:1), single-blind study conducted in patients with MPM who had received no prior chemotherapy for MPM. Patients received pemetrexed 500 mg/m^2 intravenously in combination with cisplatin 75 mg/m^2 intravenously on Day 1 of each 21-day cycle or cisplatin 75 mg/m^2 intravenously on Day 1 of each 21-day cycle administered until disease progression or unacceptable toxicity. Safety was assessed in 226 patients who received at least one dose of pemetrexed in combination with cisplatin and 222 patients who received at least one dose of cisplatin alone. Among 226 patients who received pemetrexed in combination with cisplatin, 74% (n=168) received full supplementation with folic acid and vitamin B12 during study therapy, 14% (n=32) were never supplemented, and 12% (n=26) were partially supplemented.

Study JMCH excluded patients with Karnofsky Performance Scale (KPS) of less than 70, inadequate bone marrow reserve and organ function, or a calculated creatinine clearance less than 45 mL/min. Patients unable to stop using aspirin or other non-steroidal anti-inflammatory drugs were also excluded from the study.

The data described below reflect exposure to pemetrexed in 168 patients that were fully supplemented with folic acid and vitamin B12. Median age was 60 years (range 19 to 85 years); 82% were men; 92% were White, 5% were Hispanic or Latino, 3.0% were Asian, and <1% were other ethnicities; 54% had KPS of 90-100. The median number of treatment cycles administered was 6 in the pemetrexed/cisplatin fully supplemented group and 2 in the pemetrexed/cisplatin never supplemented group. Patients receiving pemetrexed in the fully supplemented group had a relative dose intensity of 93% of the protocol-specified pemetrexed dose intensity. The most common adverse reaction resulting in dose delay was neutropenia.

Table 8 provides the frequency and severity of adverse reactions ≥ 5% in the subgroup of pemetrexed-treated patients who were fully vitamin supplemented in Study JMCH. Study JMCH was not designed to demonstrate a statistically significant reduction in adverse reaction rates for pemetrexed, as compared to the control arm, for any specified adverse reaction listed in the table below.

Table 8: Adverse Reactions Occurring in ≥ 5% of Fully Supplemented Subgroup of Patients Receiving Pemetrexed/Cisplatin in Study JMCHa

Adverse Reactionb | Pemetrexed/cisplatin (N=168) |  | Cisplatin (N=163)
Adverse Reactionb | All Grades (%) | Grade 3-4 (%) | All Grades (%) | Grade 3-4 (%)
Laboratory
Hematologic
Neutropenia | 56 | 23 | 13 | 3
Anemia | 26 | 4 | 10 | 0
Thrombocytopenia | 23 | 5 | 9 | 0
Renal
Elevated creatinine | 11 | 1 | 10 | 1
Decreased creatinine clearance | 16 | 1 | 18 | 2
Clinical
Gastrointestinal
Nausea | 82 | 12 | 77 | 6
Vomiting | 57 | 11 | 50 | 4
Stomatitis/pharyngitis | 23 | 3 | 6 | 0
Anorexia | 20 | 1 | 14 | 1
Diarrhea | 17 | 4 | 8 | 0
Constipation | 12 | 1 | 7 | 1
Dyspepsia | 5 | 1 | 1 | 0
Constitutional Symptoms
Fatigue | 48 | 10 | 42 | 9
Dermatology/Skin
Rash | 16 | 1 | 5 | 0
Alopecia | 11 | 0 | 6 | 0
Neurology
Sensory neuropathy | 10 | 0 | 10 | 1
Taste disturbance | 8 | 0 | 6 | 0
Metabolism and Nutrition
Dehydration | 7 | 4 | 1 | 1
Eye Disorder
Conjunctivitis | 5 | 0 | 1 | 0
a In Study JMCH, 226 patients received at least one dose of pemetrexed in combination with cisplatin and 222 patients received at least one dose of cisplatin. Table 8 provides the ADRs for subgroup of patients treated with pemetrexed in combination with cisplatin
(168 patients) or cisplatin alone (163 patients) who received full supplementation with folic acid and vitamin B12 during study therapy.
b NCI CTCAE version 2.0.

The following additional adverse reactions were observed in patients receiving pemetrexed plus cisplatin:

Incidence 1% to <5%

Body as a Whole — febrile neutropenia, infection, pyrexia

Dermatology/Skin — urticaria

General Disorders — chest pain

Metabolism and Nutrition — increased AST, increased ALT, increased GGT

Renal — renal failure

Incidence <1%

Cardiovascular — arrhythmia

Neurology — motor neuropathy

Exploratory Subgroup Analyses based on Vitamin Supplementation

Table 9 provides the results of exploratory analyses of the frequency and severity of NCI CTCAE Grade 3 or 4 adverse reactions reported in more pemetrexed-treated patients who did not receive vitamin supplementation (never supplemented) as compared with those who received vitamin supplementation with daily folic acid and vitamin B12 from the time of enrollment in Study JMCH (fully-supplemented).

Table 9: Exploratory Subgroup Analysis of Selected Grade 3/4 Adverse Reactions Occurring in Patients Receiving Pemetrexed in Combination with Cisplatin with or without Full Vitamin Supplementation in Study JMCHa

Grade 3-4 Adverse Reactions | Fully Supplemented Patients N=168 (%) | Never Supplemented Patients N=32 (%)
Neutropenia | 23 | 38
Thrombocytopenia | 5 | 9
Vomiting | 11 | 31
Febrile neutropenia | 1 | 9
Infection with Grade 3/4 neutropenia | 0 | 6
Diarrhea | 4 | 9
a NCI CTCAE version 2.0.

The following adverse reactions occurred more frequently in patients who were fully vitamin supplemented than in patients who were never supplemented:

- hypertension (11% versus 3%),
- chest pain (8% versus 6%),
- thrombosis/embolism (6% versus 3%).

Additional Experience Across Clinical Trials

Sepsis, with or without neutropenia, including fatal cases: 1%

Severe esophagitis, resulting in hospitalization: <1%

6.2 Postmarketing Experience

The following adverse reactions have been identified during post-approval use of pemetrexed. Because these reactions are reported voluntarily from a population of uncertain size, it is not always possible to reliably estimate their frequency or establish a causal relationship to drug exposure.

Blood and Lymphatic System — immune-mediated hemolytic anemia

Gastrointestinal — colitis, pancreatitis

General Disorders and Administration Site Conditions — edema

Injury, poisoning, and procedural complications — radiation recall

Respiratory — interstitial pneumonitis

Skin — Serious and fatal bullous skin conditions, Stevens-Johnson syndrome, and toxic epidermal necrolysis

7. DRUG INTERACTIONS

Effects of Ibuprofen on Pemetrexed

Ibuprofen increases exposure (AUC) of pemetrexed [see Clinical Pharmacology (12.3)]. In patients with creatinine clearance between 45 mL/min and 79 mL/min:

- Avoid administration of ibuprofen for 2 days before, the day of, and 2 days following administration of PEMRYDI RTU [see Dosage and Administration (2.5)].
- Monitor patients more frequently for myelosuppression, renal, and gastrointestinal toxicity, if concomitant administration of ibuprofen cannot be avoided.

8. USE IN SPECIFIC POPULATIONS

8.1 Pregnancy

Risk Summary

Based on findings from animal studies and its mechanism of action, pemetrexed can cause fetal harm when administered to a pregnant woman [see Clinical Pharmacology (12.1)]. There are no available data on pemetrexed use in pregnant women. In animal reproduction studies, intravenous administration of pemetrexed to pregnant mice during the period of organogenesis was teratogenic, resulting in developmental delays and malformations at doses lower than the recommended human dose of 500 mg/m^2 [see Data]. Advise pregnant women of the potential risk to a fetus [see Use in Special Populations (8.3)].

In the U.S. general population, the estimated background risk of major birth defects and miscarriage in clinically recognized pregnancies is 2% to 4% and 15% to 20%, respectively.

Data

Animal Data

Pemetrexed was teratogenic in mice. Daily dosing of pemetrexed by intravenous injection to pregnant mice during the period of organogenesis increased the incidence of fetal malformations (cleft palate; protruding tongue; enlarged or misshaped kidney; and fused lumbar vertebra) at doses (based on BSA) 0.03 times the human dose of 500 mg/m^2. At doses, based on BSA, greater than or equal to 0.0012 times the 500 mg/m^2 human dose, pemetrexed administration resulted in dose-dependent increases in developmental delays (incomplete ossification of talus and skull bone; and decreased fetal weight).

8.2 Lactation

Risk Summary

There is no information regarding the presence of pemetrexed or its metabolites in human milk, the effects on the breastfed child, or the effects on milk production. Because of the potential for serious adverse reactions in a breastfed child from pemetrexed injection, advise women not to breastfeed during treatment with pemetrexed injection and for one week after the last dose.

8.3 Females and Males of Reproductive Potential

Based on animal data, pemetrexed can cause malformations and developmental delays when administered to a pregnant woman [see Use in Specific Populations (8.1)].

Pregnancy Testing

Verify pregnancy status of females of reproductive potential prior to initiating Pemetrexed Injection [see Use in Specific Populations (8.1)].

Contraception

Females

Because of the potential for genotoxicity, advise females of reproductive potential to use effective contraception during treatment with pemetrexed injection and for 6 months after the last dose of pemetrexed.

Males

Because of the potential for genotoxicity, advise males with female partners of reproductive potential to use effective contraception during treatment with pemetrexed injection and for 3 months after the last dose [see Nonclinical Toxicology (13.1)].

Infertility

Males

Pemetrexed may impair fertility in males of reproductive potential. It is not known whether these effects on fertility are reversible [see Nonclinical Toxicology (13.1)].

8.4 Pediatric Use

The safety and effectiveness of pemetrexed in pediatric patients have not been established.

The safety and pharmacokinetics of pemetrexed were evaluated in two clinical studies conducted in pediatric patients with recurrent solid tumors (NCT00070473 N=32 and NCT00520936 N=72). Patients in both studies received concomitant vitamin B12 and folic acid supplementation and dexamethasone.

No tumor responses were observed. Adverse reactions observed in pediatric patients were similar to those observed in adults.

Single-dose pharmacokinetics of pemetrexed were evaluated in 22 patients age 4 to 18 years enrolled in NCT00070473 were within range of values in adults.

8.5 Geriatric Use

Of the 3,946 patients enrolled in clinical studies of pemetrexed, 34% were 65 and over and 4% were 75 and over. No overall differences in effectiveness were observed between these patients and younger patients. The incidences of Grade 3-4 anemia, fatigue, thrombocytopenia, hypertension, and neutropenia were higher in patients 65 years of age and older as compared to younger patients: in at least one of five randomized clinical trials [see Adverse Reactions (6.1) and Clinical Studies (14.1, 14.2)].

8.6 Patients with Renal Impairment

Pemetrexed is primarily excreted by the kidneys. Decreased renal function results in reduced clearance and greater exposure (AUC) to pemetrexed compared with patients with normal renal function [Warnings and Precautions (5.2, 5.6) and Clinical Pharmacology (12.3)]. No dose is recommended for patients with creatinine clearance less than 45 mL/min [see Dosage and Administration (2.3)].

10. OVERDOSAGE

No drugs are approved for the treatment of pemetrexed overdose. Based on animal studies, administration of leucovorin may mitigate the toxicities of pemetrexed overdosage. It is not known whether pemetrexed is dialyzable.

11. DESCRIPTION

Pemetrexed is a folate analog metabolic inhibitor. The drug substance, Pemetrexed Disodium Hemipentahydrate, has the chemical name disodium N-[4-[2-(2-amino-4,7-dihydro-4-oxo-1H-pyrrolo[2,3-d]pyrimidin-5-yl)ethyl] benzoyl]-L-glutamic acid hemipentahydrate, with a molecular formula of C20H19N5Na2O6•2.5 H2O and a molecular weight of 516.41. The structural formula is as follows:

PEMRYDI RTU is a sterile clear, colorless to pale yellow to green-yellow ready-to-use solution in single-dose vials. Each milliliter of solution contains 10 mg of pemetrexed (equivalent to 12.1 mg pemetrexed disodium hemipentahydrate), 10 mg of mannitol, 9 mg of sodium chloride, 1 mg of L-cysteine hydrochloride, sodium hydroxide and/or hydrochloric acid to adjust pH and water for injection.

12. CLINICAL PHARMACOLOGY

12.1 Mechanism of Action

Pemetrexed is a folate analog metabolic inhibitor that disrupts folate-dependent metabolic processes essential for cell replication. In vitro studies show that pemetrexed inhibits thymidylate synthase (TS), dihydrofolate reductase, and glycinamide ribonucleotide formyltransferase (GARFT), which are folate-dependent enzymes involved in the de novo biosynthesis of thymidine and purine nucleotides. Pemetrexed is taken into cells by membrane carriers such as the reduced folate carrier and membrane folate binding protein transport systems. Once in the cell, pemetrexed is converted to polyglutamate forms by the enzyme folylpolyglutamate synthetase. The polyglutamate forms are retained in cells and are inhibitors of TS and GARFT.

12.2 Pharmacodynamics

Pemetrexed inhibited the in vitro growth of mesothelioma cell lines (MSTO-211H, NCI-H2052) and showed synergistic effects when combined with cisplatin.

Based on population pharmacodynamic analyses, the depth of the absolute neutrophil counts (ANC) nadir correlates with the systemic exposure to pemetrexed and supplementation with folic acid and vitamin B12. There is no cumulative effect of pemetrexed exposure on ANC nadir over multiple treatment cycles.

12.3 Pharmacokinetics

Absorption

The pharmacokinetics of pemetrexed when pemetrexed injection was administered as a single agent in doses ranging from 0.2 to 838 mg/m^2 infused over a 10-minute period have been evaluated in 426 cancer patients with a variety of solid tumors. Pemetrexed total systemic exposure (AUC) and maximum plasma concentration (Cmax) increased proportionally with increase of dose. The pharmacokinetics of pemetrexed did not change over multiple treatment cycles.

Distribution

Pemetrexed has a steady-state volume of distribution of 16.1 liters. In vitro studies indicated that pemetrexed is 81% bound to plasma proteins.

Elimination

The total systemic clearance of pemetrexed is 91.8 mL/min and the elimination half-life of pemetrexed is 3.5 hours in patients with normal renal function (creatinine clearance of 90 mL/min). As renal function decreases, the clearance of pemetrexed decreases and exposure (AUC) of pemetrexed increases.

Metabolism

Pemetrexed is not metabolized to an appreciable extent.

Excretion

Pemetrexed is primarily eliminated in the urine, with 70% to 90% of the dose recovered unchanged within the first 24 hours following administration. In vitro studies indicated that pemetrexed is a substrate of OAT3 (organic anion transporter 3), a transporter that is involved in the active secretion of pemetrexed.

Specific Populations

Age (26 to 80 years) and sex had no clinically meaningful effect on the systemic exposure of pemetrexed based on population pharmacokinetic analyses.

Racial Groups

The pharmacokinetics of pemetrexed were similar in Whites and Blacks or African Americans. Insufficient data are available for other ethnic groups.

Patients with Hepatic Impairment

Pemetrexed has not been formally studied in patients with hepatic impairment. No effect of elevated AST, ALT, or total bilirubin on the PK of pemetrexed was observed in clinical studies.

Patients with Renal Impairment

Pharmacokinetic analyses of pemetrexed included 127 patients with impaired renal function. Plasma clearance of pemetrexed decreases as renal function decreases, with a resultant increase in systemic exposure. Patients with creatinine clearances of 45, 50, and 80 mL/min had 65%, 54%, and 13% increases, respectively in systemic exposure (AUC) compared to patients with creatinine clearance of 100 mL/min [see Dosage and Administration (2.3) and Warnings and Precautions (5.2)].

Third-Space Fluid

The pemetrexed plasma concentrations in patients with various solid tumors with stable, mild to moderate third-space fluid were comparable to those observed in patients without third space fluid collections. The effect of severe third space fluid on pharmacokinetics is not known.

Drug Interaction Studies

Drugs Inhibiting OAT3 Transporter

Ibuprofen, an OAT3 inhibitor, administered at 400 mg four times a day decreased the clearance of pemetrexed and increased its exposure (AUC) by approximately 20% in patients with normal renal function (creatinine clearance > 80 mL/min).

In Vitro Studies

Pemetrexed is a substrate for OAT3. Ibuprofen, an OAT3 inhibitor inhibited the uptake of pemetrexed in OAT3-expressing cell cultures with an average [Iu]/IC50 ratio of 0.38. In vitro data predict that at clinically relevant concentrations, other NSAIDs (naproxen, diclofenac, celecoxib) would not inhibit the uptake of pemetrexed by OAT3 and would not increase the AUC of pemetrexed to a clinically significant extent [see Drug Interactions (7)].

Pemetrexed is a substrate for OAT4. In vitro, ibuprofen and other NSAIDs (naproxen, diclofenac, celecoxib) are not inhibitors of OAT4 at clinically relevant concentrations.

Aspirin

Aspirin, administered in low to moderate doses (325 mg every 6 hours), does not affect the pharmacokinetics of pemetrexed.

Cisplatin

Cisplatin does not affect the pharmacokinetics of pemetrexed and the pharmacokinetics of total platinum are unaltered by pemetrexed.

Vitamins

Neither folic acid nor vitamin B12 affect the pharmacokinetics of pemetrexed.

Drugs Metabolized by Cytochrome P450 Enzymes

In vitro studies suggest that pemetrexed does not inhibit the clearance of drugs metabolized by CYP3A, CYP2D6, CYP2C9, and CYP1A2.

13. NONCLINICAL TOXICOLOGY

13.1 Carcinogenesis, Mutagenesis, Impairment of Fertility

No carcinogenicity studies have been conducted with pemetrexed. Pemetrexed was clastogenic in an in vivo micronucleus assay in mouse bone marrow but was not mutagenic in multiple in vitro tests (Ames assay, Chinese Hamster Ovary cell assay).

Pemetrexed administered intraperitoneally at doses of ≥ 0.1 mg/kg/day to male mice (approximately 0.0006 times the recommended human dose based on BSA) resulted in reduced fertility, hypospermia, and testicular atrophy.

14. CLINICAL STUDIES

14.1 Non-Squamous NSCLC

Initial Treatment in Combination with Pembrolizumab and Platinum

The efficacy of pemetrexed in combination with pembrolizumab and platinum chemotherapy was investigated in Study KEYNOTE-189 (NCT02578680), a randomized, multicenter, double-blind, active-controlled trial conducted in patients with metastatic non-squamous NSCLC, regardless of PD-L1 tumor expression status, who had not previously received systemic therapy for metastatic disease and in whom there were no EGFR or ALK genomic tumor aberrations. Patients with autoimmune disease that required systemic therapy within 2 years of treatment; a medical condition that required immunosuppression; or who had received more than 30 Gy of thoracic radiation within the prior 26 weeks were ineligible. Randomization was stratified by smoking status (never versus former/current), choice of platinum (cisplatin versus carboplatin), and tumor PD-L1 status (TPS < 1% [negative] versus TPS ≥ 1%). Patients were randomized (2:1) to one of the following treatment arms:

- Pemetrexed 500 mg/m^2, pembrolizumab 200 mg, and investigator's choice of cisplatin 75 mg/m^2 or carboplatin AUC 5 mg/mL/min intravenously on Day 1 of each 21-day cycle for 4 cycles followed by pemetrexed 500 mg/m^2 and pembrolizumab 200 mg intravenously every 3 weeks. Pemetrexed was administered after pembrolizumab and prior to platinum chemotherapy on Day 1.
- Placebo, pemetrexed 500 mg/m^2, and investigator's choice of cisplatin 75 mg/m^2 or carboplatin AUC 5 mg/mL/min intravenously on Day 1 of each 21-day cycle for 4 cycles followed by placebo and pemetrexed 500 mg/m^2 intravenously every 3 weeks.

Treatment with pemetrexed continued until RECIST v1.1 (modified to follow a maximum of 10 target lesions and a maximum of 5 target lesions per organ)-defined progression of disease as determined by the investigator or unacceptable toxicity.

Patients randomized to placebo, pemetrexed, and platinum chemotherapy were offered pembrolizumab as a single agent at the time of disease progression.

Assessment of tumor status was performed at Week 6, Week 12, and then every 9 weeks thereafter. The main efficacy outcome measures were OS and PFS as assessed by BICR RECIST v1.1, modified to follow a maximum of 10 target lesions and a maximum of five target lesions per organ. Additional efficacy outcome measures were ORR and duration of response, as assessed by the BICR according to RECIST v1.1, modified to follow a maximum of 10 target lesions and a maximum of 5 target lesions per organ.

A total of 616 patients were randomized: 410 patients to the pemetrexed, pembrolizumab, and platinum chemotherapy arm and 206 to the placebo, pemetrexed, and platinum chemotherapy arm. The study population characteristics were: median age of 64 years (range: 34 to 84); 49% age 65 or older; 59% male; 94% White and 3% Asian; 56% ECOG performance status of 1; and 18% with history of brain metastases. Thirty-one percent had tumor PD-L1 expression TPS < 1%. Seventy-two percent received carboplatin and 12% were never smokers. A total of 85 patients in the placebo, pemetrexed, and chemotherapy arm received an anti-PD-1/PD-L1 monoclonal antibody at the time of disease progression.

The trial demonstrated a statistically significant improvement in OS and PFS for patients randomized to pemetrexed in combination with pembrolizumab and platinum chemotherapy compared with placebo, pemetrexed, and platinum chemotherapy (see Table 10 and Figure 1).

Table 10: Efficacy Results of KEYNOTE-189

Endpoint | Pemetrexed; Pembrolizumab; Platinum Chemotherapy; n=410 | Placebo; Pemetrexed; Platinum Chemotherapy; n=206
OS
Number (%) of patients with event | 127 (31%) | 108 (52%)
Median in months (95% CI) | NR; (NR, NR) | 11.3; (8.7, 15.1)
Hazard ratioa (95% CI) | 0.49 (0.38, 0.64)
p-valueb | < 0.0001
PFS
Number of patients with event (%) | 245 (60%) | 166 (81%)
Median in months (95% CI) | 8.8 (7.6, 9.2) | 4.9 (4.7, 5.5)
Hazard ratioa (95% CI) | 0.52 (0.43, 0.64)
p-valueb | < 0.0001
ORR
Overall response ratec (95% CI) | 48% (43, 53) | 19% (14, 25)
Complete response | 0.5% | 0.5%
Partial response | 47% | 18%
p-valued | < 0.0001
Duration of Response
Median in months (range) | 11.2 (1.1+, 18.0+) | 7.8 (2.1+, 16.4+)
a Based on the stratified Cox proportional hazard model.
b Based on stratified log-rank test.
c Response: Best objective response as confirmed complete response or partial response.
d Based on Miettinen and Nurminen method stratified by PD-L1 status, platinum chemotherapy and smoking status.
NR = not reached

At the protocol specified final OS analysis, the median in the pemetrexed in combination with pembrolizumab and platinum chemotherapy arm was 22.0 months (95% CI: 19.5, 24.5) compared to 10.6 months (95% CI: 8.7, 13.6) in the placebo with pemetrexed and platinum chemotherapy arm, with an HR of 0.56 (95% CI: 0.46, 0.69).

Figure 1: Kaplan-Meier Curve for Overall Survival in KEYNOTE-189*

*Based on the protocol-specified final OS analysis

Initial Treatment in Combination with Cisplatin

The efficacy of pemetrexed was evaluated in Study JMDB (NCT00087711), a multi-center, randomized (1:1), open-label study conducted in 1,725 chemotherapy-naive patients with Stage IIIb/IV NSCLC. Patients were randomized to receive pemetrexed with cisplatin or gemcitabine with cisplatin. Randomization was stratified by Eastern Cooperative Oncology Group Performance Status (ECOG PS 0 versus 1), gender, disease stage, basis for pathological diagnosis (histopathological/cytopathological), history of brain metastases, and investigative center. Pemetrexed was administered intravenously over 10 minutes at a dose of 500 mg/m^2 on Day 1 of each 21-day cycle. Cisplatin was administered intravenously at a dose of 75 mg/m^2 approximately 30 minutes after pemetrexed administration on Day 1 of each cycle, gemcitabine was administered at a dose of 1,250 mg/m^2 on Day 1 and Day 8, and cisplatin was administered intravenously at a dose of 75 mg/m^2 approximately 30 minutes after administration of gemcitabine, on Day 1 of each 21-day cycle. Treatment was administered up to a total of 6 cycles; patients in both arms received folic acid, vitamin B12, and dexamethasone [see Dosage and Administration (2.4)]. The primary efficacy outcome measure was overall survival.

A total of 1,725 patients were enrolled with 862 patients randomized to pemetrexed in combination with cisplatin and 863 patients to gemcitabine in combination with cisplatin. The median age was 61 years (range 26-83 years), 70% were male, 78% were White, 17% were Asian, 2.9% were Hispanic or Latino, and 2.1% were Black or African American, and < 1% were other ethnicities. Among patients for whom ECOG PS (n=1,722) and smoking history (n=1,516) were collected, 65% had an ECOG PS of 1, 36% had an ECOG PS of 0, and 84% were smokers. For tumor characteristics, 73% had non-squamous NSCLC and 27% had squamous NSCLC; 76% had Stage IV disease. Among 1,252 patients with non-squamous NSCLC histology, 68% had a diagnosis of adenocarcinoma, 12% had large cell histology and 20% had other histologic subtypes.

Efficacy results in Study JMDB are presented in Table 11 and Figure 2.

Table 11: Efficacy Results in Study JMDB

Efficacy Parameter | Pemetrexed plus Cisplatin; (N=862) | Gemcitabine plus Cisplatin; (N=863)
Overall Survival
Median (months); (95% CI) | 10.3; (9.8-11.2) | 10.3; (9.6-10.9)
Hazard ratio (HR)a,b; (95% CI) | 0.94; (0.84-1.05)
Progression-Free Survival
Median (months); (95% CI) | 4.8; (4.6-5.3) | 5.1; (4.6-5.5)
Hazard ratio (HR)a,b; (95% CI) | 1.04; (0.94-1.15)
Overall Response Rate; (95% CI) | 27.1%; (24.2-30.1) | 24.7%; (21.8-27.6)
a Unadjusted for multiple comparisons.
b Adjusted for gender, stage, basis of diagnosis, and performance status.

Figure 2: Kaplan-Meier Curves for Overall Survival in Study JMDB

In pre-specified analyses assessing the impact of NSCLC histology on overall survival, clinically relevant differences in survival according to histology were observed. These subgroup analyses are shown in Table 12 and Figures 3 and 4. This difference in treatment effect for pemetrexed based on histology demonstrating a lack of efficacy in squamous cell histology was also observed in Studies JMEN and JMEI.

Table 12: Overall Survival in NSCLC Histologic Subgroups in Study JMDB

Histologic Subgroups | Pemetrexed plus Cisplatin; (N=862) | Gemcitabine plus Cisplatin; (N=863)
Non-squamous NSCLC (N=1,252)
Median (months); (95% CI) | 11.0; (10.1-12.5) | 10.1; (9.3-10.9)
HRa,b; (95% CI) | 0.84; (0.74-0.96)
Adenocarcinoma (N=847)
Median (months); (95% CI) | 12.6; (10.7-13.6) | 10.9; (10.2-11.9)
HRa,b; (95% CI) | 0.84; (0.71-0.99)
Large Cell (N=153)
Median (months); (95% CI) | 10.4; (8.6-14.1) | 6.7; (5.5-9.0)
HRa,b; (95% CI) | 0.67; (0.48-0.96)
Non-squamous, not otherwise specified (N=252)
Median (months); (95% CI) | 8.6; (6.8-10.2) | 9.2; (8.1-10.6)
HRa,b; (95% CI) | 1.08; (0.81-1.45)
Squamous Cell (N=473)
Median (months); (95% CI) | 9.4; (8.4-10.2) | 10.8; (9.5-12.1)
HRa,b; (95% CI) | 1.23; (1.00-1.51)
a Unadjusted for multiple comparisons.
b Adjusted for ECOG PS, gender, disease stage, and basis for pathological diagnosis (histopathological/cytopathological).

Figure 3: Kaplan-Meier Curves for Overall Survival in Non-squamous NSCLC in Study JMDB

Figure 4: Kaplan-Meier Curves for Overall Survival in Squamous NSCLC in Study JMDB

Maintenance Treatment Following First-line Non-Pemetrexed Containing Platinum-Based Chemotherapy

The efficacy of pemetrexed as maintenance therapy following first-line platinum-based chemotherapy was evaluated in Study JMEN (NCT00102804), a multicenter, randomized (2:1), double-blind, placebo-controlled study conducted in 663 patients with Stage IIIb/IV NSCLC who did not progress after four cycles of platinum-based chemotherapy. Patients were randomized to receive pemetrexed 500 mg/m^2 intravenously every 21 days or placebo until disease progression or intolerable toxicity. Patients in both study arms received folic acid, vitamin B12, and dexamethasone [see Dosage and Administration (2.4)]. Randomization was carried out using a minimization approach [Pocock and Simon (1,975)] using the following factors: gender, ECOG PS (0 versus 1), response to prior chemotherapy (complete or partial response versus stable disease), history of brain metastases (yes versus no), non-platinum component of induction therapy (docetaxel versus gemcitabine versus paclitaxel), and disease stage (IIIb versus IV). The major efficacy outcome measures were progression-free survival based on assessment by independent review and overall survival; both were measured from the date of randomization in Study JMEN.

A total of 663 patients were enrolled with 441 patients randomized to pemetrexed and 222 patients randomized to placebo. The median age was 61 years (range 26-83 years); 73% were male; 65% were White, 32% were Asian, 2.9% were Hispanic or Latino, and < 2% were other ethnicities; 60% had an ECOG PS of 1; and 73% were current or former smokers. Median time from initiation of platinum-based chemotherapy to randomization was 3.3 months (range 1.6 to 5.1 months) and 49% of the population achieved a partial or complete response to first-line, platinum-based chemotherapy. With regard to tumor characteristics, 81% had Stage IV disease, 73% had non-squamous NSCLC and 27% had squamous NSCLC. Among the 481 patients with non-squamous NSCLC, 68% had adenocarcinoma, 4% had large cell, and 28% had other histologies.

Efficacy results are presented in Table 13 and Figure 5.

Table 13: Efficacy Results in Study JMEN

Efficacy Parameter | Pemetrexed | Placebo
Overall survival | N=441 | N=222
Median (months); (95% CI) | 13.4; (11.9-15.9) | 10.6; (8.7-12.0)
Hazard ratioa; (95% CI) | 0.79; (0.65-0.95)
p-value | p=0.012
Progression-free survival per independent review | N=387 | N=194
Median (months); (95% CI) | 4.0; (3.1-4.4) | 2.0; (1.5-2.8)
Hazard ratioa; (95% CI) | 0.60; (0.49-0.73)
p-value | p < 0.00001
a Hazard ratios are adjusted for multiplicity but not for stratification variables.

Figure 5: Kaplan-Meier Curves for Overall Survival in Study JMEN

The results of pre-specified subgroup analyses by NSCLC histology are presented in Table 14 and Figures 6 and 7.

Table 14: Efficacy Results in Study JMEN by Histologic Subgroup

Efficacy Parameter | Overall Survival |  | Progression-Free Survival; Per Independent Review
Efficacy Parameter | Pemetrexed; (N=441) | Placebo; (N=222) | Pemetrexed; (N=387) | Placebo; (N=194)
Non-squamous NSCLC (n=481)
Median (months) | 15.5 | 10.3 | 4.4 | 1.8
HRa; (95% CI) | 0.70; (0.56-0.88) |  | 0.47; (0.37-0.60)
Adenocarcinoma (n=328)
Median (months) | 16.8 | 11.5 | 4.6 | 2.7
HRa; (95% CI) | 0.73; (0.56-0.96) |  | 0.51; (0.38-0.68)
Large cell carcinoma (n=20)
Median (months) | 8.4 | 7.9 | 4.5 | 1.5
HRa; (95% CI) | 0.98; (0.36-2.65) |  | 0.40; (0.12-1.29)
Otherb (n=133)
Median (months) | 11.3 | 7.7 | 4.1 | 1.6
HRa; (95% CI) | 0.61; (0.40-0.94) |  | 0.44; (0.28-0.68)
Squamous cell NSCLC (n=182)
Median (months) | 9.9 | 10.8 | 2.4 | 2.5
HRa; (95% CI) | 1.07; (0.77-1.50) |  | 1.03; (0.71-1.49)
a Hazard ratios are not adjusted for multiplicity
b Primary diagnosis of NSCLC not specified as adenocarcinoma, large cell carcinoma, or squamous cell carcinoma.

Figure 6: Kaplan-Meier Curves for Overall Survival in Non-squamous NSCLC in Study JMEN

Figure 7: Kaplan-Meier Curves for Overall Survival in Squamous NSCLC in Study JMEN

Maintenance Treatment Following First-line Pemetrexed Plus Platinum Chemotherapy

The efficacy of pemetrexed as maintenance therapy following first-line platinum-based chemotherapy was also evaluated in PARAMOUNT (NCT00789373), a multi-center, randomized (2:1), double-blind, placebo-controlled study conducted in patients with Stage IIIb/IV non-squamous NSCLC who had completed four cycles of pemetrexed in combination with cisplatin and achieved a complete response (CR) or partial response (PR) or stable disease (SD). Patients were required to have an ECOG PS of 0 or 1. Patients were randomized to receive pemetrexed 500 mg/m^2 intravenously every 21 days or placebo until disease progression. Randomization was stratified by response to pemetrexed in combination with cisplatin induction therapy (CR or PR versus SD), disease stage (IIIb versus IV), and ECOG PS (0 versus 1). Patients in both arms received folic acid, vitamin B12, and dexamethasone. The main efficacy outcome measure was investigator-assessed progression-free survival (PFS) and an additional efficacy outcome measure was overall survival (OS); PFS and OS were measured from the time of randomization.

A total of 539 patients were enrolled with 359 patients randomized to pemetrexed and 180 patients randomized to placebo. The median age was 61 years (range 32 to 83 years); 58% were male; 95% were White, 4.5% were Asian, and < 1% were Black or African American; 67% had an ECOG PS of 1; 78% were current or former smokers; and 43% of the population achieved a partial or complete response to first-line, platinum-based chemotherapy. With regard to tumor characteristics, 91% had Stage IV disease, 87% had adenocarcinoma, 7% had large cell, and 6% had other histologies.

Efficacy results for PARAMOUNT are presented in Table 15 and Figure 8.

Table 15: Efficacy Results in PARAMOUNT

Efficacy Parameter | Pemetrexed; (N=359) | Placebo; (N=180)
Overall survival
Median (months); (95% CI) | 13.9; (12.8-16.0) | 11.0; (10.0-12.5)
Hazard ratio (HR)a; (95% CI) | 0.78; (0.64-0.96)
p-value | p=0.02
Progression-free survivalb
Median (months); (95% CI) | 4.1; (3.2-4.6) | 2.8; (2.6-3.1)
Hazard ratio (HR) a; (95% CI) | 0.62; (0.49-0.79)
p-value | p < 0.0001
a Hazard ratios are adjusted for multiplicity but not for stratification variables.
b Based on investigator's assessment.

Figure 8: Kaplan-Meier Curves for Overall Survival in PARAMOUNT

Treatment of Recurrent Disease After Prior Chemotherapy

The efficacy of pemetrexed was evaluated in Study JMEI (NCT00004881), a multicenter, randomized (1:1), open-label study conducted in patients with Stage III or IV NSCLC that had recurred or progressed following one prior chemotherapy regimen for advanced disease. Patients were randomized to receive pemetrexed 500 mg/m^2 intravenously or docetaxel 75 mg/m^2 as a 1-hour intravenous infusion once every 21 days. Patients randomized to pemetrexed also received folic acid and vitamin B12. The study was designed to show that overall survival with pemetrexed was non-inferior to docetaxel, as the major efficacy outcome measure, and that overall survival was superior for patients randomized to pemetrexed compared to docetaxel, as a secondary outcome measure.

A total of 571 patients were enrolled with 283 patients randomized to pemetrexed and 288 patients randomized to docetaxel. The median age was 58 years (range 22 to 87 years); 72% were male; 71% were White, 24% were Asian, 2.8% were Black or African American, 1.8% were Hispanic or Latino, and < 2% were other ethnicities; 88% had an ECOG PS of 0 or 1. With regard to tumor characteristics, 75% had Stage IV disease; 53% had adenocarcinoma, 30% had squamous histology; 8% large cell; and 9% had other histologic subtypes of NSCLC.

The efficacy results in the overall population and in subgroup analyses based on histologic subtype are provided in Tables 16 and 17, respectively. Study JMEI did not show an improvement in overall survival in the intent-to-treat population. In subgroup analyses, there was no evidence of a treatment effect on survival in patients with squamous NSCLC; the absence of a treatment effect in patients with NSCLC of squamous histology was also observed Studies JMDB and JMEN [see Clinical Studies (14.1)].

Table 16: Efficacy Results in Study JMEI

Efficacy Parameter | Pemetrexed; (N=283) | Docetaxel; (N=288)
Overall survival
Median (months); (95% CI) | 8.3; (7.0-9.4) | 7.9; (6.3-9.2)
Hazard ratioa; (95% CI) | 0.99; (0.82-1.20)
Progression-free survival
Median (months); (95% CI) | 2.9; (2.4-3.1) | 2.9; (2.7-3.4)
Hazard ratioa; (95% CI) | 0.97; (0.82-1.16)
Overall response rate; (95% CI) | 8.5%; (5.2-11.7) | 8.3%; (5.1-11.5)
a Hazard ratios are not adjusted for multiplicity or for stratification variables.

Table 17: Exploratory Efficacy Analyses by Histologic Subgroup in Study JMEI

Histologic Subgroups | Pemetrexed; (N=283) | Docetaxel; (N=288)
Non-squamous NSCLC (N=399)
Median (months); (95% CI) | 9.3; (7.8-9.7) | 8.0; (6.3-9.3)
HRa; (95% CI) | 0.89; (0.71-1.13)
Adenocarcinoma (N=301)
Median (months); (95% CI) | 9.0; (7.6-9.6) | 9.2; (7.5-11.3)
HRa; (95% CI) | 1.09; (0.83-1.44)
Large Cell (N=47)
Median (months); (95% CI) | 12.8; (5.8-14.0) | 4.5; (2.3-9.1)
HRa; (95% CI) | 0.38; (0.18-0.78)
Otherb (N=51)
Median (months); (95% CI) | 9.4; (6.0-10.1) | 7.9; (4.0-8.9)
HRa; (95% CI) | 0.62; (0.32-1.23)
Squamous NSCLC (N=172)
Median (months); (95% CI) | 6.2; (4.9-8.0) | 7.4; (5.6-9.5)
HRa; (95% CI) | 1.32; (0.93-1.86)
a Hazard ratio unadjusted for multiple comparisons.
b Primary diagnosis of NSCLC not specified as adenocarcinoma, large cell carcinoma, or squamous cell carcinoma.

14.2 Mesothelioma

The efficacy of pemetrexed was evaluated in Study JMCH (NCT00005636), a multicenter, randomized (1:1), single-blind study conducted in patients with MPM who had received no prior chemotherapy. Patients were randomized (n=456) to receive pemetrexed 500 mg/m^2 intravenously over 10 minutes followed 30 minutes later by cisplatin 75 mg/m^2 intravenously over two hours on Day 1 of each 21-day cycle or to receive cisplatin 75 mg/m^2 intravenously over 2 hours on Day 1 of each 21-day cycle; treatment continued until disease progression or intolerable toxicity. The study was modified after randomization and treatment of 117 patients to require that all patients receive folic acid 350 mcg to 1,000 mcg daily beginning 1 to 3 weeks prior to the first dose of pemetrexed and continuing until 1 to 3 weeks after the last dose, vitamin B12 1,000 mcg intramuscularly 1 to 3 weeks prior to first dose of pemetrexed and every 9 weeks thereafter, and dexamethasone 4 mg orally, twice daily, for 3 days starting the day prior to each pemetrexed dose. Randomization was stratified by multiple baseline variables including KPS, histologic subtype (epithelial, mixed, sarcomatoid, other), and gender. The major efficacy outcome measure was overall survival and additional efficacy outcome measures were time to disease progression, overall response rate, and response duration.

A total of 448 patients received at least one dose of protocol-specified therapy; 226 patients were randomized to and received at least one dose of pemetrexed plus cisplatin, and 222 patients were randomized to and received cisplatin. Among the 226 patients who received cisplatin with pemetrexed, 74% received full supplementation with folic acid and vitamin B12 during study therapy, 14% were never supplemented, and 12% were partially supplemented. Across the study population, the median age was 61 years (range: 20 to 86 years); 81% were male; 92% were White, 5% were Hispanic or Latino, 3.1% were Asian, and < 1% were other ethnicities; and 54% had a baseline KPS score of 90-100% and 46% had a KPS score of 70-80%. With regard to tumor characteristics, 46% had Stage IV disease, 31% Stage III, 15% Stage II, and 7% Stage I disease at baseline; the histologic subtype of mesothelioma was epithelial in 68% of patients, mixed in 16%, sarcomatoid in 10% and other histologic subtypes in 6%. The baseline demographics and tumor characteristics of the subgroup of fully supplemented patients was similar to the overall study population.

The efficacy results from Study JMCH are summarized in Table 18 and Figure 9.

Table 18: Efficacy Results in Study JMCH

Efficacy Parameter | All Randomized and Treated Patients (N=448) |  | Fully Supplemented Patients (N=331)
Efficacy Parameter | Pemetrexed/Cisplatin; (N=226) | Cisplatin; (N=222) | Pemetrexed/Cisplatin; (N=168) | Cisplatin; (N=163)
Median overall survival (months) | 12.1 | 9.3 | 13.3 | 10.0
(95% CI) | (10.0-14.4) | (7.8-10.7) | (11.4-14.9) | (8.4-11.9)
Hazard ratioa | 0.77 |  | 0.75
Log rank p-value | 0.020 |  | NAb
a Hazard ratios are not adjusted for stratification variables.
b Not a pre-specified analysis.

Figure 9: Kaplan-Meier Curves for Overall Survival in Study JMCH

Based upon prospectively defined criteria (modified Southwest Oncology Group methodology) the objective tumor response rate for pemetrexed plus cisplatin was greater than the objective tumor response rate for cisplatin alone. There was also improvement in lung function (forced vital capacity) in the pemetrexed plus cisplatin arm compared to the control arm.

15. REFERENCES

1. “OSHA Hazardous Drugs” OSHA [https://www.osha.gov/hazardous-drugs].

16. HOW SUPPLIED/STORAGE AND HANDLING

How Supplied

PEMRYDI RTU (pemetrexed injection) is supplied as a sterile clear, colorless to pale yellow to green-yellow ready-to-use solution packaged in a USP type-I glass vial with rubber stopper and aluminium flip-off cap.

It is available as follows:

100 mg/10 mL (10 mg/mL):

1 Single-dose Vial in a Carton: NDC 70121-2453-1

500 mg/50 mL (10 mg/mL):

1 Single-dose Vial in a Carton: NDC 70121-2461-1

1,000 mg/100 mL (10 mg/mL):

1 Single-dose Vial in a Carton: NDC 70121-2462-1

Storage and Handling

Store at 20°C to 25°C (68°F to 77°F); excursions permitted to 15°C to 30°C (59°F to 86°F) [see USP Controlled Room Temperature].

PEMRYDI RTU is a hazardous drug. Follow applicable special handling and disposal procedures.^1

17. PATIENT COUNSELING INFORMATION

Advise the patient to read the FDA-approved patient labeling (Patient Information).

Premedication and Concomitant Medication: Instruct patients to take folic acid as directed and to keep appointments for vitamin B12 injections to reduce the risk of treatment-related toxicity. Instruct patients of the requirement to take corticosteroids to reduce the risks of treatment-related toxicity [see Dosage and Administration (2.4) and Warnings and Precautions (5.1)].

Myelosuppression: Inform patients of the risk of low blood cell counts and instruct them to immediately contact their physician for signs of infection, fever, bleeding, or symptoms of anemia [see Warnings and Precautions (5.1)].

Renal Failure: Inform patients of the risks of renal failure, which may be exacerbated in patients with dehydration arising from severe vomiting or diarrhea. Instruct patients to immediately contact their healthcare provider for a decrease in urine output [see Warnings and Precautions (5.2)].

Bullous and Exfoliative Skin Disorders: Inform patients of the risks of severe and exfoliative skin disorders. Instruct patients to immediately contact their healthcare provider for development of bullous lesions or exfoliation in the skin or mucous membranes [see Warnings and Precautions (5.3)].

Interstitial Pneumonitis: Inform patients of the risks of pneumonitis. Instruct patients to immediately contact their healthcare provider for development of dyspnea or persistent cough [see Warnings and Precautions (5.4)].

Radiation Recall: Inform patients who have received prior radiation of the risks of radiation recall. Instruct patients to immediately contact their healthcare provider for development of inflammation or blisters in an area that was previously irradiated [see Warnings and Precautions (5.5)].

Increased Risk of Toxicity with Ibuprofen in Patients with Renal Impairment: Advise patients with mild to moderate renal impairment of the risks associated with concomitant ibuprofen use and instruct them to avoid use of all ibuprofen containing products for 2 days before, the day of, and 2 days following administration of PEMRYDI RTU [see Dosage and Administration (2.5), Warnings and Precautions (5.6), and Drug Interactions (7)].

Embryo-Fetal Toxicity: Advise females of reproductive potential and males with female partners of reproductive potential of the potential risk to a fetus [see Warnings and Precautions (5.7) and Use in Specific Populations (8.1)]. Advise females of reproductive potential to use effective contraception during treatment with PEMRYDI RTU and for 6 months after the last dose. Advise females to inform their prescriber of a known or suspected pregnancy. Advise males with female partners of reproductive potential to use effective contraception during treatment with PEMRYDI RTU and for 3 months after the last dose [see Warnings and Precautions (5.7) and Use in Specific Populations (8.3)].

Lactation: Advise women not to breastfeed during treatment with PEMRYDI RTU and for 1 week after the last dose [see Use in Specific Populations (8.2)].

PEMRYDI RTU® is a registered trademark of Amneal Pharmaceuticals LLC.

Manufactured by:

Zydus Lifesciences Limited

Ahmedabad, India.

Distributed by:

Amneal Pharmaceuticals LLC

Bridgewater, NJ 08807

Rev. 07-2025-03

PATIENT INFORMATION

PEMRYDI RTU® (PEM-rih-DEE. AR. TEE. YU.)

(pemetrexed injection)

For Intravenous Use

What is PEMRYDI RTU?

PEMRYDI RTU is a prescription medicine used to treat:

- a kind of lung cancer called non-squamous non-small cell lung cancer (NSCLC). PEMRYDI RTU is used:

- as the first treatment in combination with pembrolizumab and platinum chemotherapy when your lung cancer with no abnormal EGFR or ALK gene has spread (advanced NSCLC).
- as the first treatment in combination with cisplatin when your lung cancer has spread (advanced NSCLC).
- alone as maintenance treatment after you have received 4 cycles of chemotherapy that contains platinum for first treatment of your advanced NSCLC and your cancer has not progressed.
- alone when your lung cancer has returned or spread after prior chemotherapy.

PEMRYDI RTU is not for use for the treatment of people with squamous cell non-small cell lung cancer.

- a kind of cancer called malignant pleural mesothelioma. This cancer affects the lining of the lungs and chest wall. PEMRYDI RTU is used in combination with cisplatin as the first treatment for malignant pleural mesothelioma that cannot be removed by surgery or you are not able to have surgery.

Pemetrexed has not been shown to be safe and effective in children.

Do not take PEMRYDI RTU if you have had a severe allergic reaction to any medicine that contains pemetrexed.

Before taking PEMRYDI RTU, tell your healthcare provider about all of your medical conditions, including if you:

- have kidney problems.
- have had radiation therapy.
- are pregnant or plan to become pregnant. PEMRYDI RTU can harm your unborn baby.

Females who are able to become pregnant:

Your healthcare provider will check to see if you are pregnant before you start treatment with PEMRYDI RTU.

You should use effective birth control (contraception) during treatment with PEMRYDI RTU and for 6 months after the last dose. Tell your healthcare provider right away if you become pregnant or think you are pregnant during treatment with PEMRYDI RTU.

Males with female partners who are able to become pregnant should use effective birth control (contraception) during treatment with PEMRYDI RTU and for 3 months after the last dose.

- are breastfeeding or plan to breastfeed. It is not known if pemetrexed passes into breast milk. Do not breastfeed during treatment with PEMRYDI RTU and for 1 week after the last dose.

Tell your healthcare provider about all the medicines you take, including prescription and over-the-counter medicines, vitamins, and herbal supplements.

Tell your healthcare provider if you have kidney problems and take a medicine that contains ibuprofen. You should avoid taking ibuprofen for 2 days before, the day of, and 2 days after receiving treatment with PEMRYDI RTU.

How is PEMRYDI RTU given?

- It is very important to take folic acid and vitamin B12 during your treatment with PEMRYDI RTU to lower your risk of harmful side effects.
  - Take folic acid exactly as prescribed by your healthcare provider 1 time a day, beginning 7 days (1 week) before your first dose of PEMRYDI RTU and continue taking folic acid until 21 days (3 weeks) after your last dose of PEMRYDI RTU.
  - Your healthcare provider will give you vitamin B12 injections during treatment with PEMRYDI RTU. You will get your first vitamin B12 injection 7 days (1 week) before your first dose of PEMRYDI RTU, and then every 3 cycles.
- Your healthcare provider will prescribe a medicine called corticosteroid for you to take 2 times a day for 3 days, beginning the day before each treatment with PEMRYDI RTU.
- PEMRYDI RTU is given to you by intravenous (IV) infusion into your vein. The infusion is given over 10 minutes.
- PEMRYDI RTU is usually given once every 21 days (3 weeks).

What are the possible side effects of PEMRYDI RTU?

PEMRYDI RTU can cause serious side effects, including:

- Low blood cell counts. Low blood cell counts can be severe, including low white blood cell counts (neutropenia), low platelet counts (thrombocytopenia), and low red blood cell counts (anemia). Your healthcare provider will do blood tests to check your blood cell counts regularly during your treatment with PEMRYDI RTU. Tell your healthcare provider right away if you have any signs of infection, fever, bleeding, or severe tiredness during your treatment with PEMRYDI RTU.
- Kidney problems, including kidney failure. PEMRYDI RTU can cause severe kidney problems that can lead to death. Severe vomiting or diarrhea can lead to loss of fluids (dehydration) which may cause kidney problems to become worse. Tell your healthcare provider right away if you have a decrease in amount of urine.
- Severe skin reactions. Severe skin reactions that may lead to death can happen with PEMRYDI RTU. Tell your healthcare provider right away if you develop blisters, skin sores, skin peeling, or painful sores, or ulcers in your mouth, nose, throat or genital area.
- Lung problems (pneumonitis). PEMRYDI RTU can cause serious lung problems that can lead to death. Tell your healthcare provider right away if you get any new or worsening symptoms of shortness of breath, cough, or fever.
- Radiation recall. Radiation recall is a skin reaction that can happen in people who have received radiation treatment in the past and are treated with PEMRYDI RTU. Tell your healthcare provider if you get swelling, blistering, or a rash that looks like a sunburn in an area that was previously treated with radiation.

The most common side effects of PEMRYDI RTU when given alone are:

● tiredness

● nausea

● loss of appetite

The most common side effects of PEMRYDI RTU when given with cisplatin are:

● vomiting

● low white blood cell counts (neutropenia)

● swelling or sores in your mouth or sore throat

● low platelet counts (thrombocytopenia)

● constipation

● low red blood cell counts (anemia)

The most common side effects of PEMRYDI RTU when given with pembrolizumab and platinum chemotherapy are:

● tiredness and weakness

● nausea

● constipation

● diarrhea

● loss of appetite

● rash

● vomiting

● cough

● shortness of breath

● fever

PEMRYDI RTU may cause fertility problems in males. This may affect your ability to father a child. It is not known if these effects are reversible. Talk to your healthcare provider if this is a concern for you.

Your healthcare provider will do blood tests to check for side effects during treatment with PEMRYDI RTU. Your healthcare provider may change your dose of PEMRYDI RTU, delay treatment, or stop treatment if you have certain side effects.

Tell your healthcare provider if you have any side effect that bothers you or that does not go away.

These are not all the side effects of PEMRYDI RTU. For more information, ask your healthcare provider or pharmacist.

Call your doctor for medical advice about side effects. You may report side effects to FDA at 1-800-FDA-1088.

General information about the safe and effective use of PEMRYDI RTU.

Medicines are sometimes prescribed for purposes other than those listed in a Patient Information leaflet. You can ask your pharmacist or healthcare provider for information about PEMRYDI RTU that is written for health professionals.

What are the ingredients in PEMRYDI RTU?

Active ingredient: Pemetrexed.

Inactive ingredients: Mannitol, sodium chloride, L-cysteine hydrochloride, sodium hydroxide and/or hydrochloric acid to adjust pH, and water for injection.

PEMRYDI RTU® is a registered trademark of Amneal Pharmaceuticals LLC.

Manufactured by:

Zydus Lifesciences Limited

Ahmedabad, India.
Distributed by:

Amneal Pharmaceuticals LLC

Bridgewater, NJ 08807
Rev. 07-2025-02
For more information, call 1-877-835-5472.

This Patient Information has been approved by the U.S. Food and Drug Administration.

PACKAGE LABEL.PRINCIPAL DISPLAY PANEL

NDC 70121-2453-1

PEMRYDI RTU (pemetrexed injection)

100 mg/10 mL (10 mg/mL)

For Intravenous infusion only

Rx only

Amneal Pharmaceuticals LLC

NDC 70121-2461-1

PEMRYDI RTU (pemetrexed injection)

500 mg/50 mL (10 mg/mL)

For Intravenous infusion only

Rx only

Amneal Pharmaceuticals LLC

NDC 70121-2462-1

PEMRYDI RTU (pemetrexed injection)

1,000 mg/100 mL (10 mg/mL)

For Intravenous infusion only

Rx only

Amneal Pharmaceuticals LLC